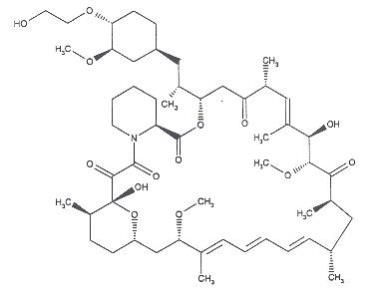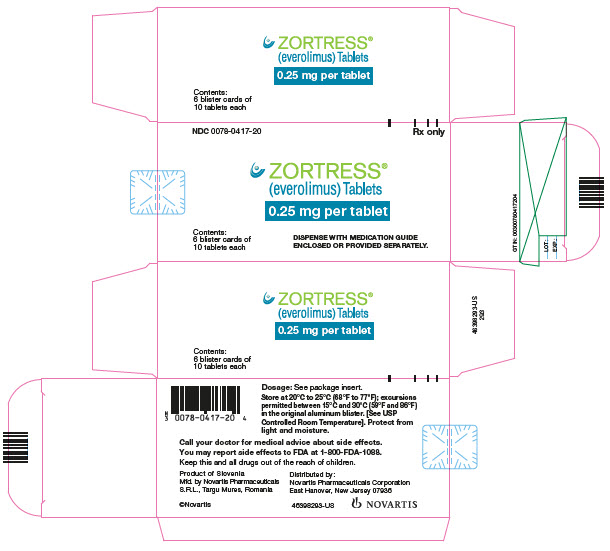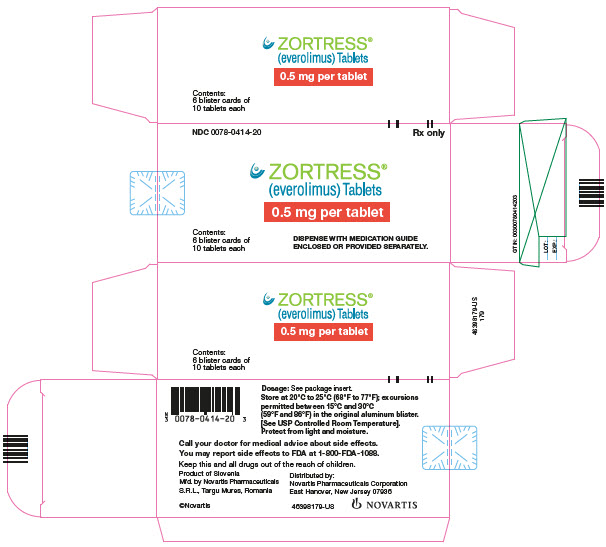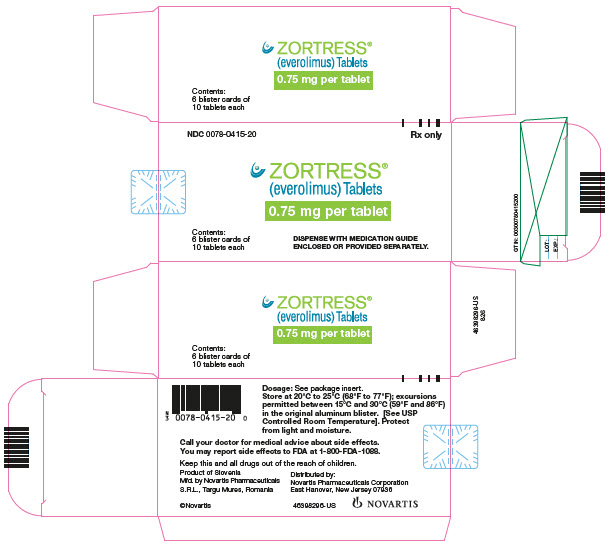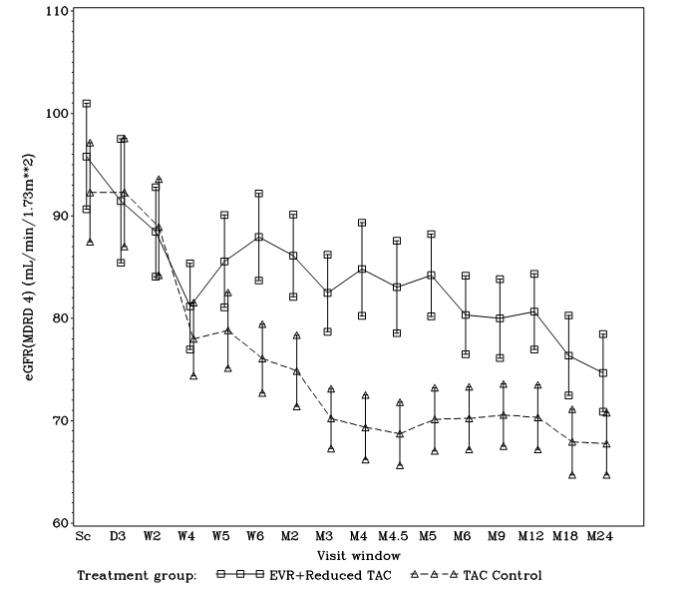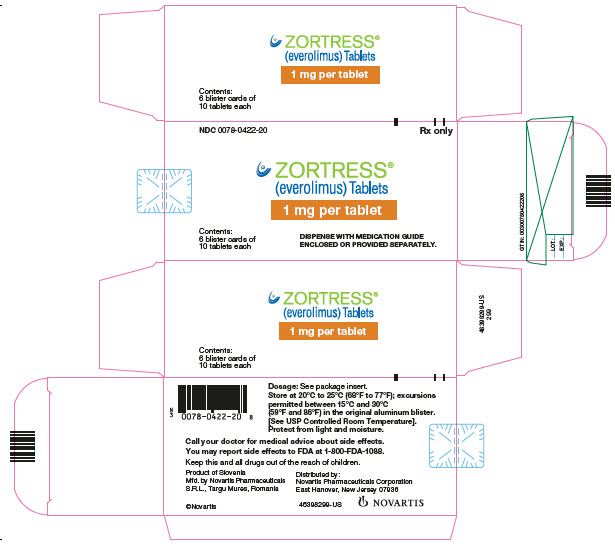 DRUG LABEL: Zortress
NDC: 0078-0417 | Form: TABLET
Manufacturer: Novartis Pharmaceuticals Corporation
Category: prescription | Type: HUMAN PRESCRIPTION DRUG LABEL
Date: 20260212

ACTIVE INGREDIENTS: EVEROLIMUS 0.25 mg/1 1
INACTIVE INGREDIENTS: BUTYLATED HYDROXYTOLUENE; CROSPOVIDONE; HYPROMELLOSES; ANHYDROUS LACTOSE; LACTOSE MONOHYDRATE; MAGNESIUM STEARATE

HIGHLIGHTS OF PRESCRIBING INFORMATION

These highlights do not include all the information needed to use ZORTRESS safely and effectively. See full prescribing information for ZORTRESS.
ZORTRESS® (everolimus) tablets, for oral use
Initial U.S. Approval: 2010

WARNING: MALIGNANCIES and SERIOUS INFECTIONS; KIDNEY GRAFT THROMBOSIS; NEPHROTOXICITY; and MORTALITY IN HEART TRANSPLANTATION

WARNING: MALIGNANCIES and SERIOUS INFECTIONS;
KIDNEY GRAFT THROMBOSIS; NEPHROTOXICITY; and
MORTALITY IN HEART TRANSPLANTATION

See full prescribing information for complete boxed warning.

- Only physicians experienced in immunosuppressive therapy and management of transplant patients should use Zortress (5.1)
- Increased susceptibility to infection and the possible development of malignancies may result from immunosuppression (5.2, 5.3)
- Increased incidence of kidney graft thrombosis (5.4)
- Reduced doses of cyclosporine are required for use in combination with Zortress in order to reduce nephrotoxicity (2.4, 2.5, 5.6, 12.7, 12.8)
- Increased mortality in a heart transplant clinical trial. Use in heart transplantation is not recommended (5.7)

RECENT MAJOR CHANGES

Warnings and Precautions, Cannabidiol Drug Interactions (5.22) | 9/2023

1 INDICATIONS AND USAGE

Zortress is an mTOR inhibitor immunosuppressant indicated for the prophylaxis of organ rejection in adult patients:

- Kidney Transplant: at low-moderate immunologic risk. Use in combination with basiliximab, cyclosporine (reduced doses) and corticosteroids (1.1)
- Liver Transplant: Administer no earlier than 30 days posttransplant. Use in combination with tacrolimus (reduced doses) and corticosteroids (1.2, 5.5)

Limitations of Use: Safety and efficacy have not been established in the following:

- Kidney transplant patients at high immunologic risk (1.3)
- Recipients of transplanted organs other than kidney or liver (1.3, 5.7)
- Pediatric patients (less than 18 years) (1.3)

2 DOSAGE AND ADMINISTRATION

- Kidney Transplantation: starting oral dose of 0.75 mg twice daily as soon as possible after transplantation (2.1)
- Liver Transplantation: starting oral dose of 1 mg twice daily starting 30 days after transplantation (2.2)
- Monitor Everolimus Concentrations: Adjust maintenance dose to achieve trough concentrations within the 3 to 8 ng/mL target range using LC/MS/MS assay method (2.1, 2.2, 2.3)
- Administer consistently with or without food at the same time as cyclosporine or tacrolimus (2.6, 12.3)
- Mild Hepatic Impairment: Reduce initial daily dose by one-third (2.7)
- Moderate or Severe Hepatic Impairment: Reduce initial daily dose by one-half (2.7, 12.6)

3 DOSAGE FORMS AND STRENGTHS

Zortress is available as 0.25 mg, 0.5 mg, 0.75 mg, and 1 mg tablets (3)

4 CONTRAINDICATIONS

- Hypersensitivity to everolimus, sirolimus, or to components of the drug product (4)

5 WARNINGS AND PRECAUTIONS

- Angioedema [increased risk with concomitant angiotensin converting enzyme (ACE inhibitors)]: Monitor for symptoms and treat promptly (5.8)
- Delayed Wound Healing/Fluid Accumulation: Monitor symptoms; treat promptly to minimize complications (5.9)
- Interstitial Lung Disease (ILD)/Non-Infectious Pneumonitis: Monitor for symptoms or radiologic changes; manage by dose reduction or discontinuation until symptoms resolve; consider use of corticosteroids (5.10)
- Hyperlipidemia (elevations of serum cholesterol and triglycerides): Monitor and consider anti-lipid therapy (5.11)
- Proteinuria (increased risk with higher trough concentrations): Monitor urine protein (5.12)
- Polyoma Virus Infections (activation of latent viral infections; BK virus associated nephropathy): Consider reducing immunosuppression (5.13)
- TMA/TTP/HUS (concomitant use with cyclosporine may increase risk): Monitor for hematologic changes or symptoms (5.15)
- New Onset Diabetes After Transplantation: Monitor serum glucose (5.16)
- Male Infertility: Azoospermia or oligospermia may occur (5.18, 13.1)
- Immunizations: Avoid live vaccines (5.19)
- Embryo-Fetal Toxicity: Advise females of reproductive potential of the potential risk to a fetus and to use effective contraception during treatment with Zortress and for 8 weeks after final dose (5.17, 8.1, 8.3)

6 ADVERSE REACTIONS

Most common adverse reactions were as follows:

- Kidney Transplantation (incidence greater than or equal to 20%): peripheral edema, constipation, hypertension, nausea, anemia, urinary tract infection (UTI), and hyperlipidemia (6.1)
- Liver Transplantation (incidence greater than 10%): diarrhea, headache, peripheral edema, hypertension, nausea, pyrexia, abdominal pain, leukopenia, and hypercholesterolemia (6.1)

To report SUSPECTED ADVERSE REACTIONS, contact Novartis Pharmaceuticals Corporation at 1-888-669-6682 or FDA at 1-800-FDA-1088 or www.fda.gov/medwatch.

7 DRUG INTERACTIONS

Strong-moderate CYP3A4 inhibitors (e.g., cyclosporine, ketoconazole, erythromycin, verapamil) and CYP3A4 inducers (e.g., rifampin) may affect everolimus concentrations (7.1). Consider Zortress dose adjustment (5.14)

Therapeutic drug monitoring and dose reduction for Zortress should be considered when Zortress is coadministered with cannabidiol (5.22, 7.13)

8 USE IN SPECIFIC POPULATIONS

- Pregnancy: Based on animal data, may cause maternal and fetal harm (8.1)
- Lactation: Breastfeeding not recommended (8.2)
- Females and Males of Reproductive Potential: May impair fertility (8.1, 8.3, 13.1)

FULL PRESCRIBING INFORMATION

WARNING: MALIGNANCIES and SERIOUS INFECTIONS; KIDNEY GRAFT THROMBOSIS; NEPHROTOXICITY; and MORTALITY IN HEART TRANSPLANTATION

Malignancies and Serious Infections

- Only physicians experienced in immunosuppressive therapy and management of transplant patients should prescribe Zortress. Patients receiving the drug should be managed in facilities equipped and staffed with adequate laboratory and supportive medical resources. The physician responsible for maintenance therapy should have complete information requisite for the follow-up of the patient [see Warnings and Precautions (5.1)].
- Increased susceptibility to infection and the possible development of malignancies, such as lymphoma and skin cancer, may result from immunosuppression [see Warnings and Precautions (5.2, 5.3)].

Kidney Graft Thrombosis

- An increased risk of kidney arterial and venous thrombosis, resulting in graft loss, was reported, mostly within the first 30 days posttransplantation [see Warnings and Precautions (5.4)].

Nephrotoxicity

- Increased nephrotoxicity can occur with use of standard doses of cyclosporine in combination with Zortress. Therefore, reduced doses of cyclosporine should be used in combination with Zortress in order to reduce renal dysfunction. It is important to monitor the cyclosporine and everolimus whole blood trough concentrations [see Dosage and Administration (2.4, 2.5), Warnings and Precautions (5.6), Clinical Pharmacology (12.7, 12.8)].

Mortality in Heart Transplantation

- Increased mortality, often associated with serious infections, within the first three months posttransplantation was observed in a clinical trial of de novo heart transplant patients receiving immunosuppressive regimens with or without induction therapy. Use in heart transplantation is not recommended [see Warnings and Precautions (5.7)].

1 INDICATIONS AND USAGE

1.1 Prophylaxis of Organ Rejection in Kidney Transplantation

Zortress is indicated for the prophylaxis of organ rejection in adult patients at low to moderate immunologic risk receiving a kidney transplant [see Clinical Studies (14.1)]. Zortress is to be administered in combination with basiliximab induction and concurrently with reduced doses of cyclosporine and with corticosteroids. Therapeutic drug monitoring (TDM) of everolimus and cyclosporine is recommended for all patients receiving these products [see Dosage and Administration (2.2, 2.3)].

1.2 Prophylaxis of Organ Rejection in Liver Transplantation

Zortress is indicated for the prophylaxis of allograft rejection in adult patients receiving a liver transplant. Zortress is to be administered no earlier than 30 days posttransplant concurrently in combination with reduced doses of tacrolimus and with corticosteroids [see Warnings and Precautions (5.5), Clinical Studies (14.2)]. TDM of everolimus and tacrolimus is recommended for all patients receiving these products [see Dosage and Administration (2.3, 2.5)].

1.3 Limitations of Use

The safety and efficacy of Zortress has not been established in the following populations:

- Kidney transplant patients at high immunologic risk.
- Recipients of transplanted organs other than kidney and liver [see Warnings and Precautions (5.7)].
- Pediatric patients (less than 18 years).

2 DOSAGE AND ADMINISTRATION

Patients receiving Zortress may require dose adjustments based on everolimus blood concentrations achieved, tolerability, individual response, change in concomitant medications and the clinical situation. Optimally, dose adjustments of Zortress should be based on trough concentrations obtained 4 or 5 days after a previous dosing change. Dose adjustment is required if the trough concentration is below 3 ng/mL. The total daily dose of Zortress should be doubled using the available tablet strengths (0.25 mg, 0.5 mg, 0.75 mg, or 1 mg). Dose adjustment is also required if the trough concentration is greater than 8 ng/mL on 2 consecutive measures; the dose of Zortress should be decreased by 0.25 mg twice daily [see Dosage and Administration (2.3), Clinical Pharmacology (12.3)].

2.1 Dosage in Adult Kidney Transplant Patients

An initial Zortress dose of 0.75 mg orally twice daily (1.5 mg per day) is recommended for adult kidney transplant patients in combination with reduced-dose cyclosporine, administered as soon as possible after transplantation [see Dosage and Administration (2.3, 2.4), Clinical Studies (14.1)].

Oral prednisone should be initiated once oral medication is tolerated. Steroid doses may be further tapered on an individualized basis depending on the clinical status of patient and function of graft.

2.2 Dosage in Adult Liver Transplant Patients

Start Zortress at least 30 days posttransplant. An initial dose of 1 mg orally twice daily (2 mg per day) is recommended for adult liver transplant patients in combination with reduced-dose tacrolimus [see Dosage and Administration (2.3, 2.5), Clinical Studies (14.2)].

Steroid doses may be further tapered on an individualized basis depending on the clinical status of patient and function of graft.

2.3 Therapeutic Drug Monitoring (TDM) - Everolimus

Routine everolimus whole blood therapeutic drug concentration monitoring is recommended for all patients. The recommended everolimus therapeutic range is 3 to 8 ng/mL [see Clinical Pharmacology (12.7)]. Careful attention should be made to clinical signs and symptoms, tissue biopsies, and laboratory parameters. It is important to monitor everolimus blood concentrations, in patients with hepatic impairment, during concomitant administration of CYP3A4 inducers or inhibitors or cannabidiol, when switching cyclosporine formulations and/or when cyclosporine dosing is reduced according to recommended target concentrations [see Drug Interactions (7), Clinical Pharmacology (12.7, 12.8)].

There is an interaction of cyclosporine on everolimus, and consequently, everolimus concentrations may decrease if cyclosporine exposure is reduced. There is little to no pharmacokinetic interaction of tacrolimus on everolimus, and thus, everolimus concentrations do not decrease if the tacrolimus exposure is reduced [see Drug Interactions (7.2)].

The everolimus recommended therapeutic range of 3 to 8 ng/mL is based on an LC/MS/MS assay method. Currently in clinical practice, everolimus whole blood trough concentrations may be measured by chromatographic or immunoassay methodologies. Because the measured everolimus whole blood trough concentrations depend on the assay used, individual patient sample concentration values from different assays may not be interchangeable. Consideration of assay results must be made with knowledge of the specific assay used. Therefore, communication should be maintained with the laboratory performing the assay.

2.4 Therapeutic Drug Monitoring (TDM) - Cyclosporine in Kidney Transplant Patients

Both cyclosporine doses and the target range for whole blood trough concentrations should be reduced, when given in a regimen with Zortress, in order to minimize the risk of nephrotoxicity [see Warnings and Precautions (5.6), Drug Interactions (7.2), Clinical Pharmacology (12.8)].

The recommended cyclosporine therapeutic ranges when administered with Zortress are 100 to 200 ng/mL through Month 1 posttransplant, 75 to 150 ng/mL at Months 2 and 3 posttransplant, 50 to 100 ng/mL at Month 4 posttransplant, and 25 to 50 ng/mL from Month 6 through Month 12 posttransplant. The median trough concentrations observed in the clinical trial ranged between 161 to 185 ng/mL through Month 1 posttransplant and between 111 to 140 ng/mL at Months 2 and 3 posttransplant. The median trough concentration was 99 ng/mL at Month 4 posttransplant and ranged between 46 to 75 ng/mL from Months 6 through Month 12 posttransplant [see Clinical Pharmacology (12.8), Clinical Studies (14.1)].

Cyclosporine, USP Modified is to be administered as oral capsules twice daily unless cyclosporine oral solution or intravenous administration of cyclosporine cannot be avoided. Cyclosporine, USP Modified should be initiated as soon as possible, and no later than 48 hours after reperfusion of the graft and dose adjusted to target concentrations from Day 5 onwards.

If impairment of renal function is progressive, the treatment regimen should be adjusted. In renal transplant patients, the cyclosporine dose should be based on cyclosporine whole blood trough concentrations [see Clinical Pharmacology (12.8)].

In renal transplantation, there are limited data regarding dosing Zortress with reduced cyclosporine trough concentrations of 25 to 50 ng/mL after 12 months. Zortress has not been evaluated in clinical trials with other formulations of cyclosporine. Prior to dose reduction of cyclosporine, it should be ascertained that steady-state everolimus whole blood trough concentration is at least 3 ng/mL. There is an interaction of cyclosporine on everolimus, and consequently, everolimus concentrations may decrease if cyclosporine exposure is reduced [see Drug Interactions (7.2)].

2.5 Therapeutic Drug Monitoring (TDM) – Tacrolimus in Liver Transplant Patients

Both tacrolimus doses and the target range for whole blood trough concentrations should be reduced, when given in a regimen with Zortress, in order to minimize the potential risk of nephrotoxicity [see Warnings and Precautions (5.6), Clinical Pharmacology (12.9)].

The recommended tacrolimus therapeutic range when administered with Zortress are whole blood trough (C-0h) concentrations of 3 to 5 ng/mL by three weeks after the first dose of Zortress (approximately Month 2) and through Month 12 posttransplant.

The median tacrolimus trough concentrations observed in the clinical trial ranged between 8.6 to 9.5 ng/mL at Weeks 2 and 4 posttransplant (prior to initiation of everolimus). The median tacrolimus trough concentrations ranged between 7 to 8.1 ng/mL at Weeks 5 and 6 posttransplant, between 5.2 to 5.6 ng/mL at Months 2 and 3 posttransplant, and between 4.3 to 4.9 ng/mL between Months 4 and 12 posttransplant [see Clinical Pharmacology (12.9), Clinical Studies (14.2)].

Tacrolimus is to be administered as oral capsules twice daily unless intravenous administration of tacrolimus cannot be avoided.

In liver transplant patients, the tacrolimus dose should be based on tacrolimus whole blood trough concentrations [see Clinical Pharmacology (12.9)].

In liver transplantation, there are limited data regarding dosing Zortress with reduced tacrolimus trough concentrations of 3 to 5 ng/mL after 12 months. Prior to dose reduction of tacrolimus, it should be ascertained that the steady-state everolimus whole blood trough concentration is at least 3 ng/mL. Unlike the interaction between cyclosporine and everolimus, tacrolimus does not affect everolimus trough concentrations, and consequently, everolimus concentrations do not decrease if the tacrolimus exposure is reduced.

2.6 Administration

Zortress tablets should be swallowed whole with a glass of water and not crushed before use.

Administer Zortress consistently approximately 12 hours apart with or without food to minimize variability in absorption and at the same time as cyclosporine or tacrolimus [see Clinical Pharmacology (12.3)].

2.7 Hepatic Impairment

Whole blood trough concentrations of everolimus should be closely monitored in patients with impaired hepatic function. For patients with mild hepatic impairment (Child-Pugh Class A), the initial daily dose should be reduced by approximately one-third of the normally recommended daily dose. For patients with moderate or severe hepatic impairment (Child-Pugh Class B or C), the initial daily dose should be reduced to approximately one-half of the normally recommended daily dose. Further dose adjustment and/or dose titration should be made if a patient’s whole blood trough concentration of everolimus, as measured by an LC/MS/MS assay, is not within the target trough concentration range of 3 to 8 ng/mL [see Clinical Pharmacology (12.6)].

3 DOSAGE FORMS AND STRENGTHS

Zortress is available as 0.25 mg, 0.5 mg, 0.75 mg, and 1 mg tablets.

Table 1. Description of Zortress (everolimus) Tablets
Dosage strength | 0.25 mg | 0.5 mg | 0.75 mg | 1 mg
Appearance | White to yellowish, marbled, round, flat tablets with beveled edge
Imprint | “C” on one side and “NVR” on the other | “CH” on one side and “NVR” on the other | “CL” on one side and “NVR” on the other | “CU” on one side and “NVR” on the other

4 CONTRAINDICATIONS

4.1 Hypersensitivity Reactions

Zortress is contraindicated in patients with known hypersensitivity to everolimus, sirolimus, or to components of the drug product.

5 WARNINGS AND PRECAUTIONS

5.1 Management of Immunosuppression

Only physicians experienced in management of systemic immunosuppressant therapy in transplantation should prescribe Zortress. Patients receiving the drug should be managed in facilities equipped and staffed with adequate laboratory and supportive medical resources. The physician responsible for the maintenance therapy should have complete information requisite for the follow-up of the patient. In limited data with the complete elimination of calcineurin inhibition (CNI), there was an increased risk of acute rejection.

5.2 Lymphomas and Other Malignancies

Patients receiving immunosuppressants, including Zortress, are at increased risk of developing lymphomas and other malignancies, particularly of the skin. The risk appears to be related to the intensity and duration of immunosuppression rather than to the use of any specific agent.

As usual for patients with increased risk for skin cancer, exposure to sunlight and ultraviolet light should be limited by wearing protective clothing and using a sunscreen with a high protection factor.

5.3 Serious Infections

Patients receiving immunosuppressants, including Zortress, are at increased risk of developing bacterial, viral, fungal, and protozoal infections, including opportunistic infections [see Warnings and Precautions (5.13), Adverse Reactions (6.1, 6.2)]. These infections may lead to serious, including fatal, outcomes. Because of the danger of over-immunosuppression, which can cause increased susceptibility to infection, combination immunosuppressant therapy should be used with caution.

Antimicrobial prophylaxis for Pneumocystis jiroveci (carinii) pneumonia and prophylaxis for cytomegalovirus (CMV) is recommended in transplant recipients.

5.4 Kidney Graft Thrombosis

An increased risk of kidney arterial and venous thrombosis, resulting in graft loss, has been reported, usually within the first 30 days posttransplantation [see Boxed Warning].

5.5 Hepatic Artery Thrombosis

Mammalian target of rapamycin (mTOR) inhibitors are associated with an increase in hepatic artery thrombosis (HAT). Reported cases mostly have occurred within the first 30 days posttransplant and most also lead to graft loss or death. Therefore, Zortress should not be administered earlier than 30 days after liver transplant.

5.6 Zortress and Calcineurin Inhibitor-Induced Nephrotoxicity

In kidney transplant recipients, Zortress with standard dose cyclosporine increases the risk of nephrotoxicity resulting in a lower glomerular filtration rate. Reduced doses of cyclosporine are required for use in combination with Zortress in order to reduce renal dysfunction [see Boxed Warning, Indications and Usage (1.1), Clinical Pharmacology (12.8)].

In liver transplant recipients, Zortress has not been studied with standard dose tacrolimus. Reduced doses of tacrolimus should be used in combination with Zortress in order to minimize the potential risk of nephrotoxicity [see Indications and Usage (1.2), Clinical Pharmacology (12.9)].

Renal function should be monitored during the administration of Zortress. Consider switching to other immunosuppressive therapies if renal function does not improve after dose adjustments or if the dysfunction is thought to be drug related. Caution should be exercised when using other drugs which are known to impair renal function.

5.7 Heart Transplantation

In a clinical trial of de novo heart transplant patients, Zortress in an immunosuppressive regimen, with or without induction therapy, resulted in an increased mortality often associated with serious infections within the first three months posttransplantation compared to the control regimen. Use of Zortress in heart transplantation is not recommended.

5.8 Angioedema

Zortress has been associated with the development of angioedema. The concomitant use of Zortress with other drugs known to cause angioedema, such as angiotensin converting enzyme (ACE) inhibitors may increase the risk of developing angioedema.

5.9 Wound Healing and Fluid Accumulation

Zortress increases the risk of delayed wound healing and increases the occurrence of wound-related complications like wound dehiscence, wound infection, incisional hernia, lymphocele and seroma. These wound-related complications may require more surgical intervention. Generalized fluid accumulation, including peripheral edema (e.g., lymphoedema) and other types of localized fluid collection, such as pericardial and pleural effusions and ascites have also been reported.

5.10 Interstitial Lung Disease (ILD)/Non-Infectious Pneumonitis

A diagnosis of interstitial lung disease (ILD) should be considered in patients presenting with symptoms consistent with infectious pneumonia but not responding to antibiotic therapy and in whom infectious, neoplastic and other non-drug causes have been ruled out through appropriate investigations. Cases of ILD, implying lung intraparenchymal inflammation (pneumonitis) and/or fibrosis of non-infectious etiology, some reported with pulmonary hypertension [including pulmonary arterial hypertension (PAH)] as a secondary event, have occurred in patients receiving rapamycins and their derivatives, including Zortress. Most cases generally resolve on drug interruption with or without glucocorticoid therapy. However, fatal cases have also occurred.

5.11 Hyperlipidemia

Increased serum cholesterol and triglycerides, requiring the need for anti-lipid therapy, have been reported to occur following initiation of Zortress and the risk of hyperlipidemia is increased with higher everolimus whole blood trough concentrations [see Adverse Reactions (6.2)]. Use of anti-lipid therapy may not normalize lipid levels in patients receiving Zortress.

Any patient who is administered Zortress should be monitored for hyperlipidemia. If detected, interventions, such as diet, exercise, and lipid-lowering agents should be initiated as outlined by the National Cholesterol Education Program guidelines. The risk/benefit should be considered in patients with established hyperlipidemia before initiating an immunosuppressive regimen containing Zortress. Similarly, the risk/benefit of continued Zortress therapy should be reevaluated in patients with severe refractory hyperlipidemia. Zortress has not been studied in patients with baseline cholesterol levels greater than 350 mg/dL.

Due to an interaction with cyclosporine, clinical trials of Zortress and cyclosporine in kidney transplant patients strongly discouraged patients from receiving the HMG-CoA reductase inhibitors simvastatin and lovastatin. During Zortress therapy with cyclosporine, patients administered an HMG-CoA reductase inhibitor and/or fibrate should be monitored for the possible development of rhabdomyolysis and other adverse effects, as described in the respective labeling for these agents [see Drug Interactions (7.7)].

5.12 Proteinuria

The use of Zortress in transplant patients has been associated with increased proteinuria. The risk of proteinuria increased with higher everolimus whole blood trough concentrations. Patients receiving Zortress should be monitored for proteinuria [see Adverse Reactions (6.2)].

5.13 Polyoma Virus Infections

Patients receiving immunosuppressants, including Zortress, are at increased risk for opportunistic infections, including polyoma virus infections. Polyoma virus infections in transplant patients may have serious, and sometimes fatal, outcomes. These include polyoma virus-associated nephropathy (PVAN), mostly due to BK virus infection, and JC virus associated progressive multiple leukoencephalopathy (PML). PVAN has been observed in patients receiving immunosuppressants, including Zortress. PVAN is associated with serious outcomes; including deteriorating renal function and kidney graft loss [see Adverse Reactions (6.2)]. Patient monitoring may help detect patients at risk for PVAN. Reductions in immunosuppression should be considered for patients who develop evidence of PVAN or PML. Physicians should also consider the risk that reduced immunosuppression represents to the functioning allograft.

5.14 Interaction With Strong Inhibitors and Inducers of CYP3A4

Coadministration of Zortress with strong CYP3A4 inhibitors (e.g., ketoconazole, itraconazole, voriconazole, clarithromycin, telithromycin, ritonavir, boceprevir, telaprevir) or strong CYP3A4 inducers (e.g., rifampin, rifabutin) is not recommended without close monitoring of everolimus whole blood trough concentrations [see Drug Interactions (7)].

5.15 Thrombotic Microangiopathy/Thrombotic Thrombocytopenic Purpura/Hemolytic Uremic Syndrome

The concomitant use of Zortress with cyclosporine may increase the risk of thrombotic microangiopathy (TMA)/thrombotic thrombocytopenic purpura (TTP)/hemolytic uremic syndrome (HUS). Monitor hematologic parameters [see Adverse Reactions (6.2)].

5.16 New Onset Diabetes After Transplant

Zortress has been shown to increase the risk of new onset diabetes mellitus after transplant. Blood glucose concentrations should be monitored closely in patients using Zortress.

5.17 Embryo-Fetal Toxicity

Based on animal studies and the mechanism of action [see Clinical Pharmacology (12.1)], Zortress may cause fetal harm when administered to a pregnant woman. In animal studies, everolimus caused embryo-fetal toxicity when administered during the period of organogenesis at maternal exposures that were equal to or less than human exposures at the recommended lowest starting dose. Advise pregnant women of the potential risk to a fetus. Advise female patients of reproductive potential to avoid becoming pregnant and to use effective contraception while using Zortress and for 8 weeks after ending treatment [see Use in Specific Populations (8.1, 8.3)].

5.18 Male Infertility

Azoospermia or oligospermia may be observed [see Adverse Reactions (6.2), Nonclinical Toxicology (13.1)]. Zortress is an anti-proliferative drug and affects rapidly dividing cells like the germ cells.

5.19 Immunizations

The use of live vaccines should be avoided during treatment with Zortress; examples include (not limited to) the following: intranasal influenza, measles, mumps, rubella, oral polio, BCG, yellow fever, varicella, and TY21a typhoid vaccines.

5.20 Interaction With Grapefruit Juice

Grapefruit and grapefruit juice inhibit cytochrome P450 3A4 and P-gp activity and should therefore be avoided with concomitant use of Zortress and cyclosporine or tacrolimus.

5.21 Patients With Hereditary Disorders/Other

Patients with rare hereditary problems of galactose intolerance, the Lapp lactase deficiency or glucose-galactose malabsorption should not take Zortress as this may result in diarrhea and malabsorption.

5.22 Cannabidiol Drug Interactions

When cannabidiol and Zortress are coadministered, closely monitor for an increase in everolimus blood levels and for adverse reactions suggestive of everolimus toxicity. A dose reduction of Zortress should be considered as needed when Zortress is coadministered with cannabidiol [see Dosage and Administration (2.3), Drug Interactions (7.13)].

6 ADVERSE REACTIONS

6.1 Serious and Otherwise Important Adverse Reactions

The following adverse reactions are discussed in greater detail in other sections of the label.

- Hypersensitivity Reactions [see Contraindications (4.1)]
- Lymphomas and Other Malignancies [see Boxed Warning, Warnings and Precautions (5.2)]
- Serious Infections [see Warnings and Precautions (5.3)]
- Kidney Graft Thrombosis [see Warnings and Precautions (5.4)]
- Hepatic Artery Thrombosis [see Warnings and Precautions (5.5)]
- Zortress and Calcineurin Inhibitor-Induced Nephrotoxicity [see Warnings and Precautions (5.6)]
- Heart Transplantation [see Warnings and Precautions (5.7)]
- Angioedema [see Warnings and Precautions (5.8)]
- Wound Healing and Fluid Accumulation [see Warnings and Precautions (5.9)]
- Interstitial Lung Disease/Non-Infectious Pneumonitis [see Warnings and Precautions (5.10)]
- Hyperlipidemia [see Warnings and Precautions (5.11)]
- Proteinuria [see Warnings and Precautions (5.12)]
- Polyoma Virus Infections [see Warnings and Precautions (5.13)]
- Thrombotic Microangiopathy/Thrombotic Thrombocytopenic Purpura/Hemolytic Uremic Syndrome (TMA/TTP/HUS) [see Warnings and Precautions (5.15)]
- New Onset Diabetes After Transplant [see Warnings and Precautions (5.16)]
- Male Infertility [see Warnings and Precautions (5.18)]

6.2 Clinical Trials Experience

Because clinical trials are conducted under widely varying conditions, the adverse reaction rates observed cannot be directly compared to rates in other trials and may not reflect the rates observed in clinical practice.

Kidney Transplantation

The data described below reflect exposure to Zortress in an open-label, randomized trial of de novo kidney transplant patients of concentration-controlled everolimus at an initial Zortress starting dose of 1.5 mg per day [target trough concentrations 3 to 8 ng/mL with reduced exposure cyclosporine (N = 274) compared to mycophenolic acid (N = 273) with standard exposure cyclosporine]. All patients received basiliximab induction therapy and corticosteroids. The population was between 18 and 70 years, more than 43% were 50 years of age or older (mean age was 46 years in the Zortress group, 47 years control group); a majority of recipients were male (64% in the Zortress group, 69% control group); and a majority of patients were Caucasian (70% in the Zortress group, 69% control group). Demographic characteristics were comparable between treatment groups. The most frequent diseases leading to transplantation were balanced between groups and included hypertension/nephrosclerosis, glomerulonephritis/glomerular disease and diabetes mellitus. Significantly more patients discontinued Zortress 1.5 mg per day treatment (83/277, 30%) than discontinued the control regimen (60/277, 22%). Of those patients who prematurely discontinued treatment, most discontinuations were due to adverse reactions: 18% in the Zortress group compared to 9% in the control group (p-value = 0.004). This difference was more prominent between treatment groups among female patients. In those patients discontinuing study medication, adverse reactions were collected up to 7 days after study medication discontinuation and serious adverse reactions up to 30 days after study medication discontinuation.

Discontinuation of Zortress at a higher dose (3 mg per day) was 95/279, 34%, including 20% due to adverse reactions, and this regimen is not recommended (see below).

The overall incidences of serious adverse reactions were 57% (159/278) in the Zortress group and 52% (141/273) in the mycophenolic acid group. Infections and infestations reported as serious adverse reactions had the highest incidence in both groups [20% (54/274) in the Zortress group and 25% (69/273) in the control group]. The difference was mainly due to the higher incidence of viral infections in the mycophenolic acid group, mainly CMV and BK virus infections. Injury, poisoning and procedural complications reported as serious adverse reactions had the second highest incidence in both groups [14% (39/274) in the Zortress group and 12% (32/273) in the control group] followed by renal and urinary disorders [10% (28/274) in the Zortress group and 13% (36/273) in the control group] and vascular disorders [10% (26/274) in the Zortress group and 7% (20/273) in the control group].

A total of 13 patients died during the first 12 months of study; 7 (3%) in the Zortress group and 6 (2%) in the control group. The most common causes of death across the study groups were related to cardiac conditions and infections.

There were 12 (4%) graft losses in the Zortress group and 8 (3%) in the control group over the 12-month study period. Of the graft losses, 4 were due to renal artery and two due to renal vein thrombosis in the Zortress group (2%) compared to two renal artery thromboses in the control group (1%) [see Boxed Warning, Warnings and Precautions (5.4)].

The most common (greater than or equal to 20%) adverse reactions observed in the Zortress group were: peripheral edema, constipation, hypertension, nausea, anemia, urinary tract infection, and hyperlipidemia.

Infections

The overall incidence of bacterial, fungal and viral infections reported as adverse reactions was higher in the control group (68%) compared to the Zortress group (64%) and was primarily due to an increased number of viral infections (21% in the control group and 10% in the Zortress group). The incidence of CMV infections reported as adverse reactions was 8% in the control group compared to 1% in the Zortress group; and 3% of the serious CMV infections in the control group versus 0% in the Zortress group were considered serious [see Warnings and Precautions (5.3)].

BK Virus

BK virus infections were lower in incidence in the Zortress group (2 patients, 1%) compared to the control group (11 patients, 4%). One of the two BK virus infections in the Zortress group, and two of the 11 BK virus infections in the control group were also reported as serious adverse reactions. BK virus infections did not result in graft loss in any of the groups in the clinical trial.

Wound Healing and Fluid Collections

Wound healing-related reactions were identified through a retrospective search and request for additional data. The overall incidence of wound-related reactions, including lymphocele, seroma, hematoma, dehiscence, incisional hernia, and infections was 35% in the Zortress group compared to 26% in the control group. More patients required intraoperative repair debridement or drainage of incisional wound complications and more required drainage of lymphoceles and seromas in the Zortress group compared to control.

Adverse reactions due to major fluid collections such as edema and other types of fluid collections was 45% in the Zortress group and 40% in the control group [see Warnings and Precautions (5.9)].

Neoplasms

Adverse reactions due to malignant and benign neoplasms were reported in 3% of patients in the Zortress group and 6% in the control group. The most frequently reported neoplasms in the control group were basal cell carcinoma, squamous cell carcinoma, skin papilloma and seborrheic keratosis. One patient in the Zortress group who underwent a melanoma excision prior to transplantation died due to metastatic melanoma [see Boxed Warning, Warnings and Precautions (5.2)].

New Onset Diabetes Mellitus (NODM)

NODM reported based on adverse reactions and random serum glucose values, was 9% in the Zortress group compared to 7% in the control group.

Endocrine Effects in Males

In the Zortress group, serum testosterone levels significantly decreased while the FSH levels significantly increased without significant changes being observed in the control group. In both the Zortress and the control groups mean testosterone and FSH levels remained within the normal range with the mean FSH level in the Zortress group being at the upper limit of the normal range (11.1 U/L). More patients were reported with erectile dysfunction in the Zortress treatment group compared to the control group (5% compared to 2%, respectively).

Table 2 compares the incidence of treatment-emergent adverse reactions reported with an incidence of greater than or equal to 10% for patients receiving Zortress with reduced dose cyclosporine or mycophenolic acid with standard dose cyclosporine. Within each MedDRA system organ class, the adverse reactions are presented in order of decreasing frequency.

Table 2. Incidence Rates of Frequent (Greater Than or Equal to 10% in Any Treatment Group) Adverse Reactions (Safety Population*)
Adverse reactions | Zortress (everolimus) 1.5 mg with reduced exposure cyclosporine N = 274 n (%) | Mycophenolic acid 1.44 g with standard exposure cyclosporine N = 273 n (%)
Any adverse reactions* | 271 (99) | 270 (99)
Blood lymphatic system disorders | 93 (34) | 111 (41)
Anemia | 70 (26) | 68 (25)
Leukopenia | 8 (3) | 33 (12)
Gastrointestinal disorders | 196 (72) | 207 (76)
Constipation | 105 (38) | 117 (43)
Nausea | 79 (29) | 85 (31)
Diarrhea | 51 (19) | 54 (20)
Vomiting | 40 (15) | 60 (22)
Abdominal pain | 36 (13) | 42 (15)
Dyspepsia | 12 (4) | 31 (11)
Abdominal pain upper | 9 (3) | 30 (11)
General disorders and administrative-site conditions | 181 (66) | 160 (59)
Edema peripheral | 123 (45) | 108 (40)
Pyrexia | 51 (19) | 40 (15)
Fatigue | 25 (9) | 28 (10)
Infections and infestations | 169 (62) | 185 (68)
Urinary tract infection | 60 (22) | 63 (23)
Upper respiratory tract infection | 44 (16) | 49 (18)
Injury, poisoning and procedural complications | 163 (60) | 163 (60)
Incision-site pain | 45 (16) | 47 (17)
Procedural pain | 40 (15) | 37 (14)
Investigations | 137 (50) | 133 (49)
Blood creatinine increased | 48 (18) | 59 (22)
Metabolism and nutrition disorders | 222 (81) | 199 (73)
Hyperlipidemia | 57 (21) | 43 (16)
Hyperkalemia | 49 (18) | 48 (18)
Hypercholesterolemia | 47 (17) | 34 (13)
Dyslipidemia | 41 (15) | 24 (9)
Hypomagnesemia | 37 (14) | 40 (15)
Hypophosphatemia | 35 (13) | 35 (13)
Hyperglycemia | 34 (12) | 38 (14)
Hypokalemia | 32 (12) | 32 (12)
Musculoskeletal and connective tissue disorders | 112 (41) | 105 (39)
Pain in extremity | 32 (12) | 29 (11)
Back pain | 30 (11) | 28 (10)
Nervous system disorders | 92 (34) | 109 (40)
Headache | 49 (18) | 40 (15)
Tremor | 23 (8) | 38 (14)
Psychiatric disorders | 90 (33) | 72 (26)
Insomnia | 47 (17) | 43 (16)
Renal and urinary disorders | 112 (41) | 124 (45)
Hematuria | 33 (12) | 33 (12)
Dysuria | 29 (11) | 28 (10)
Respiratory, thoracic and mediastinal disorders | 86 (31) | 93 (34)
Cough | 20 (7) | 30 (11)
Vascular disorders | 122 (45) | 124 (45)
Hypertension | 81 (30) | 82 (30)
*The safety analysis population defined as all randomized kidney transplant patients who received at least one dose of treatment and had at least one post-baseline safety assessment.

Adverse reaction that occurred with at least a 5% higher frequency in the Zortress 1.5 mg group compared to the control group were: peripheral edema (45% compared to 40%), hyperlipidemia (21% compared to 16%), dyslipidemia (15% compared to 9%), and stomatitis/mouth ulceration (8% compared to 3%).

A third treatment group of Zortress 3 mg per day (1.5 mg twice daily; target trough concentrations 6 to 12 ng/mL) with reduced exposure cyclosporine was included in the study described above. Although as effective as the lower dose Zortress group, the overall safety was worse and consequently higher doses of Zortress cannot be recommended. Out of 279 patients, 95 (34%) discontinued the study medication with 57 (20%) doing so because of adverse reactions. The most frequent adverse reactions leading to discontinuation of Zortress when used at this higher dose were injury, poisoning and procedural complications (Zortress 1.5 mg: 5%, Zortress 3 mg: 7%, and control: 2%), infections (2%, 6%, and 3%, respectively), renal and urinary disorders (4%, 7%, and 4%, respectively), and gastrointestinal disorders (1%, 3%, and 2%).

The combination of fixed-dose Zortress and standard doses of cyclosporine in previous kidney clinical trials resulted in frequent elevations of serum creatinine with higher mean and median serum creatinine values observed than in the current study with reduced exposure cyclosporine. These results indicate that Zortress increases the cyclosporine-induced nephrotoxicity, and, therefore, should only be used in a concentration-controlled regimen with reduced exposure cyclosporine [see Boxed Warning, Indications and Usage (1.1), Warnings and Precautions (5.6)].

Liver Transplantation

The data described below reflect exposure to Zortress starting 30 days after transplantation in an open-label, randomized trial of liver transplant patients. Seven hundred and nineteen (719) patients who fulfilled the inclusion/exclusion criteria [see Clinical Studies (14.2)] were randomized into one of the three treatment groups of the study. During the first 30 days prior to randomization, patients received tacrolimus and corticosteroids, with or without mycophenolate mofetil (about 70% to 80% received MMF). No induction antibody was administered. At randomization, MMF was discontinued and patients were randomized to Zortress initial dose of 1 mg twice per day (2 mg daily) and adjusted to protocol specified target trough concentrations of 3 to 8 ng/mL with reduced exposure tacrolimus [protocol-specified target troughs 3 to 5 ng/mL] (N = 245) [see Clinical Pharmacology (12.7, 12.9)] or to a control group of standard exposure tacrolimus [protocol-specified target troughs 8 to 12 ng/mL up to Month 4 posttransplant, then 6 to 10 ng/mL Month 4 through Month 12 posttransplant] (N = 241). A third randomized group was discontinued prematurely [see Clinical Studies (14.2)] and is not described in this section.

The population was between 18 and 70 years, more than 50% were 50 years of age (mean age was 54 years in the Zortress group, 55 years in the tacrolimus control group); 74% were male in both Zortress and control groups, respectively, and a majority were Caucasian (86% Zortress group, 80% control group). Demographic characteristics were comparable between treatment groups. The most frequent diseases leading to transplantation were balanced between groups. The most frequent causes of end-stage liver disease (ESLD) were alcoholic cirrhosis, hepatitis C, and hepatocellular carcinoma and were balanced between groups.

Twenty-seven percent (27%) discontinued study drug in the Zortress group compared with 22% for the tacrolimus control group during the first 12 months of study. The most common reason for discontinuation of study medication was due to adverse reactions (19% and 11%, respectively), including proteinuria, recurrent hepatitis C, and pancytopenia in the Zortress group. At 24 months, the rate of discontinuation of study medication in liver transplant patients was greater for the Zortress group (42%) compared to tacrolimus control group (33%).

The overall incidences of serious adverse reactions were 50% (122/245) in the Zortress group and 43% (104/241) in the control group at 12 months and similar at 24 months (56% and 54%, respectively). Infections and infestations were reported as serious adverse reactions with the highest incidence followed by gastrointestinal disorders and hepatobiliary disorders.

During the first 12 months of study, 13 deaths were reported in the Zortress group (one patient never took Zortress). In the same 12-month period, 7 deaths were reported in the tacrolimus control group. Deaths occurred in both groups for a variety of reasons and were mostly associated with liver-related issues, infections and sepsis. In the following 12 months of study, four additional deaths were reported in each treatment group.

The most common adverse reactions (reported for greater or equal to 10% patients in any group) in the Zortress group were: diarrhea, headache, peripheral edema, hypertension, nausea, pyrexia, abdominal pain, and leukopenia (see Table 3).

Infections

The overall incidence of infections reported as adverse reactions was 50% for Zortress and 44% in the control group and similar at 24 months (56% and 52%, respectively). The types of infections were reported as follows: bacterial 16% vs 12%, viral 17% vs 13%; and fungal infections 2% vs 5% for Zortress and control, respectively [see Warnings and Precautions (5.3)].

Wound Healing and Fluid Collections

Wound healing complications were reported as adverse reactions for 11% of patients in the Zortress group compared to 8% of patients in the control group up to 24 months. Pleural effusions were reported in 5% in both groups, and ascites in 4% of patients in the Zortress group and 3% in the control arm.

Neoplasms

Malignant and benign neoplasms were reported as adverse reactions in 4% of patients in the Zortress group and 7% in the control group at 12 months. In the Zortress group, 3 malignant tumors were reported compared to 9 cases in the control group. For the Zortress group this included lymphoma, lymphoproliferative disorder and a hepatocellular carcinoma, and for the control group included Kaposi’s sarcoma (2), metastatic colorectal cancer, glioblastoma, malignant hepatic neoplasm, pancreatic neuroendocrine tumor, hemophagocytic histiocytosis, and squamous cell carcinomas. At 24 months, the rates of malignancies were similar (10% and 11%, respectively) [see Boxed Warning, Warnings and Precautions (5.2)].

Lipid Abnormalities

Hyperlipidemia adverse reactions (including the preferred terms: hyperlipidemia, hypercholesterolemia, blood cholesterol increased, blood triglycerides increased, hypertriglyceridemia lipids increased, total cholesterol/HDL ratio increased, and dyslipidemia) were reported for 24% Zortress patients, and 10% control patients at 12 months. Results were similar at 24 months (28% and 12%, respectively).

New Onset of Diabetes after Transplant (NODAT)

Of the patients without diabetes mellitus at randomization, NODAT was reported in 32% in the Zortress group compared to 29% in the control group at 12 months and similar at 24 months.

Table 3 compares the incidence of treatment-emergent adverse reactions reported with an incidence of greater than or equal to 10% for patients receiving Zortress with reduced exposure tacrolimus or standard dose tacrolimus from randomization to 24 months. Within each MedDRA system organ class, the adverse reactions are presented in order of decreasing frequency.

Table 3. Incidence Rates of Most Frequent (Greater Than or Equal to 10% in Any Treatment Group) Adverse Reactions at 12 Months and 24 Months After Liver Transplantation (Safety Population*)
Adverse reactions | 12 months |  | 24 months
 | Zortress with reduced exposure tacrolimus N = 245 n (%) | Tacrolimus standard exposure N = 241 n (%) | Zortress with reduced exposure tacrolimus N = 245 n (%) | Tacrolimus standard exposure N = 242 n (%)
Any adverse reaction/infection | 232 (95) | 229 (95) | 236 (96) | 237 (98)
Blood & lymphatic system disorders | 66 (27) | 47 (20) | 79 (32) | 58 (24)
-Leukopenia | 29 (12) | 12 (5) | 31 (13) | 12 (5)
Gastrointestinal disorders | 136 (56) | 121 (50) | 148 (60) | 138 (57)
-Diarrhea | 47 (19) | 50 (21) | 59 (24) | 61 (25)
-Nausea | 33 (14) | 28 (12) | 36 (15) | 33 (14)
-Abdominal pain | 32 (13) | 22 (9) | 37 (15) | 31 (13)
General disorders and administration site conditions | 94 (38) | 85 (35) | 113 (46) | 98 (41)
-Peripheral edema | 43 (18) | 26 (11) | 49 (20) | 31 (13)
-Pyrexia | 32 (13) | 25 (10) | 43 (18) | 28 (12)
-Fatigue | 22 (9) | 26 (11) | 27 (11) | 28 (12)
Infections and infestations | 123 (50) | 105 (44) | 135 (56) | 125 (52)
-Hepatitis C** | 28 (11) | 19 (8) | 33 (14) | 24 (10)
Investigations | 81 (33) | 78 (32) | 92 (38) | 98 (41)
-Liver function test abnormal | 16 (7) | 24 (10) | 19 (8) | 25 (10)
Metabolism and nutrition disorders | 111 (45) | 92 (38) | 134 (55) | 106 (44)
-Hypercholesterolemia | 23 (9) | 6 (3) | 27 (11) | 9 (4)
Nervous system disorders | 89 (36) | 85 (35) | 99 (40) | 101 (42)
-Headache | 47 (19) | 46 (19) | 53 (22) | 54 (22)
-Tremor | 23 (9) | 29 (12) | 25 (10) | 37 (15)
-Insomnia | 14 (6) | 19 (8) | 17 (7) | 24 (10)
Renal and urinary disorders | 49 (20) | 53 (22) | 67 (27) | 73 (30)
-Renal failure | 13 (5) | 17 (7) | 24 (10) | 37 (15)
Vascular disorders | 56 (23) | 57 (24) | 72 (29) | 68 (28)
-Hypertension | 42 (17) | 38 (16) | 52 (21) | 44 (18)
*The safety analysis population is defined as all randomized liver transplant patients who received at least one dose of treatment and had at least one post-baseline safety assessment.
Primary system organ classes are presented alphabetically.
**No de novo hepatitis C cases were reported.

Less Common Adverse Reactions

Less common adverse reactions, occurring overall in greater than or equal to 1% to less than 10% of either kidney or liver transplant patients treated with Zortress include:

Blood and Lymphatic System Disorders: anemia, leukocytosis, lymphadenopathy, neutropenia, pancytopenia, thrombocythemia, thrombocytopenia

Cardiac and Vascular Disorders: angina pectoris, atrial fibrillation, cardiac failure congestive, palpitations, tachycardia, hypertension, including hypertensive crisis, hypotension, deep-vein thrombosis

Endocrine Disorders: Cushingoid, hyperparathyroidism, hypothyroidism

Eye Disorders: cataract, conjunctivitis, vision blurred

Gastrointestinal Disorders: abdominal distention, abdominal hernia, ascites, constipation, dyspepsia, dysphagia, epigastric discomfort, flatulence, gastritis, gastroesophageal reflux disease, gingival hypertrophy, hematemesis, hemorrhoids, ileus, mouth ulceration, peritonitis, stomatitis

General Disorders and Administrative Site Conditions: chest discomfort, chest pain, chills, fatigue, incisional hernia, inguinal hernia, malaise, edema, including generalized edema, pain

Hepatobiliary Disorders: hepatic enzyme increased, bile duct stenosis, bilirubin increased, cholangitis, cholestasis, hepatitis (non-infectious)

Infections and Infestations: BK virus infection [see Warnings and Precautions (5.13)], bacteremia, bronchitis, candidiasis, cellulitis, CMV, folliculitis, gastroenteritis, herpes infections, influenza, lower respiratory tract, nasopharyngitis, onychomycosis, oral candidiasis, oral herpes, osteomyelitis, pneumonia, pyelonephritis, sepsis, sinusitis, tinea pedis, upper respiratory tract infection, urethritis, urinary tract infection, wound infection [see Boxed Warning, Warnings and Precautions (5.3)]

Injury Poisoning and Procedural Complications: incision site complications, including infections, perinephric collection, seroma, wound dehiscence, incisional hernia, perinephric hematoma, localized intra-abdominal fluid collection, impaired healing, lymophocele, lymphorrhea

Investigations: blood alkaline phosphatase increased, blood creatinine increased, blood glucose increased, hemoglobin decreased, white blood cell count decreased, transaminases increased

Metabolism and Nutrition Disorders: blood urea increased, acidosis, anorexia, dehydration, diabetes mellitus [see Warnings and Precautions (5.16)], decreased appetite, fluid retention, gout, hypercalcemia, hypertriglyceridemia, hyperuricemia, hypocalcemia, hypokalemia, hypoglycemia, hypomagnesemia, hyponatremia, iron deficiency, new onset diabetes mellitus, vitamin B12 deficiency

Musculoskeletal and Connective Tissues Disorders: arthralgia, joint swelling, muscle spasms, muscular weakness, musculoskeletal pain, myalgia, osteoarthritis, osteonecrosis, osteopenia, osteoporosis, spondylitis

Nervous System Disorders: dizziness, hemiparesis, hypoesthesia, lethargy, migraine, neuralgia, paresthesia, somnolence, syncope, tremor

Psychiatric Disorders: agitation, anxiety, depression, hallucination

Renal and Urinary Disorders: bladder spasm, hydronephrosis, micturation urgency, nephritis interstitial, nocturia, pollakiuria, polyuria, proteinuria [see Warnings and Precautions (5.12)], pyuria, renal artery thrombosis [see Boxed Warning, Warnings and Precautions (5.4)], acute renal failure, renal impairment [see Warnings and Precautions (5.6)], renal tubular necrosis, urinary retention

Reproductive System and Breast Disorders: amenorrhea, benign prostatic hyperplasia, erectile dysfunction, ovarian cyst, scrotal edema

Respiratory, Thoracic, Mediastinal Disorders: atelectasis, bronchitis, dyspnea, cough, epistaxis, lower respiratory tract infection, nasal congestion, oropharyngeal pain, pleural effusions, pulmonary edema, rhinorrhea, sinus congestion, wheezing

Skin and Subcutaneous Tissue Disorders: acne, alopecia, dermatitis acneiform, ecchymosis, hirsutism, hyperhidrosis, hypertrichosis, night sweats, pruritus, rash

Vascular Disorders: venous thromboembolism (including deep vein thrombosis), phlebitis, pulmonary embolism

Less common, serious adverse reactions occurring overall in less than 1% of either kidney or liver transplant patients treated with Zortress include:

- Angioedema [see Warnings and Precautions (5.8)]
- Interstitial Lung Disease/Non-Infectious Pneumonitis [see Warnings and Precautions (5.10), Adverse Reactions (6.1)]
- Pericardial Effusions [see Warnings and Precautions (5.9)]
- Pancreatitis
- Thrombotic Microangiopathy (TMA), Thrombotic Thrombocytopenic Purpura (TTP), and Hemolytic Uremic Syndrome (HUS) [see Warnings and Precautions (5.15)]

6.3 Postmarketing Experience

Adverse reactions identified from the postmarketing use of the combination regimen of Zortress and cyclosporine that are not specific to any one transplant indication include angioedema [see Warnings and Precautions (5.8)], erythroderma, leukocytoclastic vasculitis, pancreatitis, pulmonary alveolar proteinosis, and pulmonary embolism. There have also been reports of male infertility with mTOR inhibitors, including Zortress [see Warnings and Precautions (5.18)].

7 DRUG INTERACTIONS

7.1 Interactions With Strong Inhibitors or Inducers of CYP3A4 and P-glycoprotein

Everolimus is mainly metabolized by CYP3A4 in the liver and to some extent in the intestinal wall and is a substrate for the multidrug efflux pump, P-glycoprotein (P-gp). Therefore, absorption and subsequent elimination of systemically absorbed everolimus may be influenced by medicinal products that affect CYP3A4 and/or P-gp. Concurrent treatment with strong inhibitors (e.g., ketoconazole, itraconazole, voriconazole, clarithromycin, telithromycin, ritonavir, boceprevir, telaprevir) and inducers (e.g., rifampin, rifabutin) of CYP3A4 is not recommended. Inhibitors of P-gp (e.g., digoxin, cyclosporine) may decrease the efflux of everolimus from intestinal cells and increase everolimus blood concentrations. In vitro, everolimus was a competitive inhibitor of CYP3A4 and of CYP2D6, potentially increasing the concentrations of medicinal products eliminated by these enzymes. Thus, caution should be exercised when coadministering Zortress with CYP3A4 and CYP2D6 substrates with a narrow therapeutic index [see Dosage and Administration (2.3)].

All in vivo interaction studies were conducted without concomitant cyclosporine. Pharmacokinetic interactions between Zortress and concomitantly administered drugs are discussed below. Drug interaction studies have not been conducted with drugs other than those described below.

7.2 Cyclosporine (CYP3A4/P-gp Inhibitor and CYP3A4 Substrate)

The steady-state Cmax and area under the curve (AUC) estimates of everolimus were significantly increased by coadministration of single dose cyclosporine [see Clinical Pharmacology (12.5)]. Dose adjustment of Zortress might be needed if the cyclosporine dose is altered [see Dosage and Administration (2.3)]. Zortress had a clinically minor influence on cyclosporine pharmacokinetics in transplant patients receiving cyclosporine (Neoral).

7.3 Ketoconazole and Other Strong CYP3A4 Inhibitors

Multiple-dose ketoconazole administration to healthy volunteers significantly increased single dose estimates of everolimus Cmax, AUC, and half-life. It is recommended that strong inhibitors of CYP3A4 (e.g., ketoconazole, itraconazole, voriconazole, clarithromycin, telithromycin, ritonavir, boceprevir, telaprevir) should not be coadministered with Zortress [see Warnings and Precautions (5.14), Clinical Pharmacology (12.5)].

7.4 Erythromycin (Moderate CYP3A4 Inhibitor)

Multiple-dose erythromycin administration to healthy volunteers significantly increased single dose estimates of everolimus Cmax, AUC, and half-life. If erythromycin is coadministered, everolimus blood concentrations should be monitored and a dose adjustment made as necessary [see Clinical Pharmacology (12.5)].

7.5 Verapamil (CYP3A4 and P-gp Substrate)

Multiple-dose verapamil administration to healthy volunteers significantly increased single dose estimates of everolimus Cmax and AUC. Everolimus half-life was not changed. If verapamil is coadministered, everolimus blood concentrations should be monitored and a dose adjustment made as necessary [see Clinical Pharmacology (12.5)].

7.6 Atorvastatin (CYP3A4 Substrate) and Pravastatin (P-gp Substrate)

Single-dose administration of Zortress with either atorvastatin or pravastatin to healthy subjects did not influence the pharmacokinetics of atorvastatin, pravastatin and everolimus, as well as total HMG-CoA reductase bioreactivity in plasma to a clinically relevant extent. However, these results cannot be extrapolated to other HMG-CoA reductase inhibitors. Patients should be monitored for the development of rhabdomyolysis and other adverse reactions as described in the respective labeling for these products.

7.7 Simvastatin and Lovastatin

Due to an interaction with cyclosporine, clinical studies of Zortress with cyclosporine conducted in kidney transplant patients strongly discouraged patients with receiving HMG-CoA reductase inhibitors such as simvastatin and lovastatin [see Warnings and Precautions (5.11)].

7.8 Rifampin (Strong CYP3A4/P-gp Inducers)

Pretreatment of healthy subjects with multiple-dose rifampin followed by a single dose of Zortress increased everolimus clearance and decreased the everolimus Cmax and AUC estimates. Combination with rifampin is not recommended [see Warnings and Precautions (5.14), Clinical Pharmacology (12.5)].

7.9 Midazolam (CYP3A4/5 Substrate)

Single-dose administration of midazolam to healthy volunteers following administration of multiple-dose Zortress indicated that everolimus is a weak inhibitor of CYP3A4/5. Dose adjustment of midazolam or other CYP3A4/5 substrates is not necessary when Zortress is coadministered with midazolam or other CYP3A4/5 substrates [see Clinical Pharmacology (12.5)].

7.10 Other Possible Interactions

Moderate inhibitors of CYP3A4 and P-gp may increase everolimus blood concentrations (e.g., fluconazole; macrolide antibiotics; nicardipine, diltiazem; nelfinavir, indinavir, amprenavir). Inducers of CYP3A4 may increase the metabolism of everolimus and decrease everolimus blood concentrations (e.g., St. John’s Wort [Hypericum perforatum]; anticonvulsants: carbamazepine, phenobarbital, phenytoin; efavirenz, nevirapine).

7.11 Octreotide

Coadministration of everolimus and depot octreotide increased octreotide Cmin by approximately 50%.

7.12 Tacrolimus

There is little to no pharmacokinetic interaction of tacrolimus on everolimus, and consequently, dose adjustment of Zortress is not necessary when Zortress is coadministered with tacrolimus.

7.13 Cannabidiol

The blood levels of everolimus may increase upon concomitant use with cannabidiol. When cannabidiol and Zortress are coadministered, closely monitor for an increase in everolimus blood levels and for adverse reactions suggestive of everolimus toxicity. A dose reduction of Zortress should be considered as needed when Zortress is coadministered with cannabidiol [see Dosage and Administration (2.3), Warnings and Precautions (5.22)].

8 USE IN SPECIFIC POPULATIONS

8.1 Pregnancy

Risk Summary

Based on animal studies and the mechanism of action [see Clinical Pharmacology (12.1)], Zortress can cause fetal harm when administered to a pregnant woman. There are limited case reports of Zortress use in pregnant women; however, these reports are insufficient to inform a drug-associated risk of adverse developmental outcomes. Reproductive studies in animals have demonstrated that everolimus was maternally toxic in rabbits and caused embryo-fetal toxicities in rats and rabbits, at exposures near or below those achieved in human transplant patients. Advise pregnant women of the potential risk to a fetus.

The background risk of major birth defects and miscarriage for the indicated population is unknown; however, in the U.S. general population, the estimated background risk of major birth defects is 2% to 4% and of miscarriage is 15% to 20% of clinically recognized pregnancies.

Data

Animal Data

Everolimus crossed the placenta and was toxic to the conceptus.

Everolimus administered daily to pregnant rats by oral gavage at 0.1 mg/kg (approximately one tenth the exposure in humans administered the lowest starting dose of 0.75 mg twice daily), from before mating through organogenesis, resulted in increased preimplantation loss and embryonic resorptions. These effects occurred in the absence of maternal toxicities.

Everolimus administered daily by oral gavage to pregnant rabbits during organogenesis resulted in abortions, maternal toxicity and lethality, and increased fetal resorptions. At these doses, exposure to everolimus (AUC) was approximately one-tenth-, one-half-, and one- and one-half-fold the exposures in humans administered the starting clinical dose, respectively.

In a pre- and post-natal development study in rats, animals were dosed from implantation through lactation. At a dose of 0.1 mg/kg (0.6 mg/m^2), there were no adverse effects on delivery and lactation or signs of maternal toxicity; however, there were reductions in body weight (up to 9% reduction) and in survival of offspring (~5%). There were no drug-related effects on the developmental parameters (morphological development, motor activity, learning, or fertility assessment) in the offspring.

8.2 Lactation

Risk Summary

There is no data regarding the presence of Zortress in human milk, the effects on breastfed infants, or the effects on milk production. Everolimus and/or its metabolites are readily transferred into milk of lactating rats at a concentration 3.5 times higher than in maternal rat serum. In pre-post-natal and juvenile studies in rats, exposure to everolimus during the postnatal period caused developmental toxicity [see Use in Specific Populations (8.1), Nonclinical Toxicology (13.2)]. Advise lactating women not to breastfeed because of the potential for serious adverse reactions in infants exposed to everolimus.

8.3 Females and Males of Reproductive Potential

Contraception

Females should not be pregnant or become pregnant while receiving Zortress. Advise females of reproductive potential that animal studies have been performed showing Zortress to be harmful to the mother and developing fetus [see Use in Specific Populations (8.1)]. Females of reproductive potential are recommended to use highly effective contraception methods while receiving Zortress and up to 8 weeks after treatment has been stopped.

Infertility

Females

Amenorrhea occurred in female patients taking Zortress [see Adverse Reactions (6.2)]. Zortress may cause pre-implantation loss in females based on animal data [see Nonclinical Toxicology (13.1)].

Female fertility may be compromised by treatment with Zortress.

Males

Zortress treatment may impair fertility in males based on human [see Warnings and Precautions (5.18), Adverse Reactions (6.2, 6.3)] and animal findings [see Nonclinical Toxicology (13.1)].

8.4 Pediatric Use

The safe and effective use of Zortress in kidney or liver transplant patients younger than 18 years of age has not been established.

8.5 Geriatric Use

There is limited clinical experience on the use of Zortress in patients of age 65 years or older. There is no evidence to suggest that elderly patients will require a different dosage recommendation from younger adult patients [see Clinical Pharmacology (12.5)].

8.6 Hepatic Impairment

Everolimus whole blood trough concentrations should be closely monitored in patients with impaired hepatic function. For patients with mild hepatic impairment (Child-Pugh Class A), the dose should be reduced by approximately one-third of the normally recommended daily dose. For patients with moderate or severe hepatic impairment (Child-Pugh Class B or C), the initial daily dose should be reduced to approximately half of the normally recommended daily dose. Further dose adjustment and/or dose titration should be made if a patient’s whole blood trough concentration of everolimus, as measured by an LC/MS/MS assay, is not within the target trough concentration range of 3 to 8 ng/mL [see Clinical Pharmacology (12.6)].

8.7 Renal Impairment

No dose adjustment is needed in patients with renal impairment [see Clinical Pharmacology (12.6)].

10 OVERDOSAGE

Reported experience with overdose in humans is very limited. There is a single case of an accidental ingestion of 1.5 mg everolimus in a 2-year-old child where no adverse reactions were observed. Single doses up to 25 mg have been administered to transplant patients with acceptable acute tolerability. Single doses up to 70 mg (without cyclosporine) have been given with acceptable acute tolerability. General supportive measures should be followed in all cases of overdose. Everolimus is not considered dialyzable to any relevant degree (less than 10% of everolimus removed within 6 hours of hemodialysis). In animal studies, everolimus showed a low acute toxic potential. No lethality or severe toxicity was observed after single oral doses of 2000 mg/kg (limit test) in either mice or rats.

11 DESCRIPTION

Zortress (everolimus) is a macrolide immunosuppressant.

The chemical name of everolimus is (1R, 9S, 12S, 15R, 16E, 18R, 19R, 21R, 23S, 24E, 26E, 28E, 30S, 32S, 35R)-1, 18-dihydroxy-12 -{(1R)-2-[(1S,3R,4R)-4-(2-hydroxyethoxy)-3-methoxycyclohexyl]-1-methylethyl}-19,30-dimethoxy-15, 17, 21, 23, 29, 35-hexamethyl-11, 36-dioxa-4-aza-tricyclo[30.3.1.0^4,9] hexatriaconta-16,24,26,28-tetraene-2, 3,10,14,20-pentaone.

The molecular formula is C53H83NO14 and the molecular weight is 958.25 g/mol. The structural formula is:

Zortress is supplied as tablets for oral administration containing 0.25 mg, 0.5 mg, 0.75 mg, and 1 mg of everolimus together with butylated hydroxytoluene, crospovidone, hypromellose, lactose anhydrous, lactose monohydrate, and magnesium stearate as inactive ingredients.

12 CLINICAL PHARMACOLOGY

12.1 Mechanism of Action

Everolimus inhibits antigenic and interleukin (IL-2 and IL-15) stimulated activation and proliferation of T and B lymphocytes.

In cells, everolimus binds to a cytoplasmic protein, the FK506 Binding Protein-12 (FKBP-12), to form an immunosuppressive complex (everolimus: FKBP-12) that binds to and inhibits the mammalian target of rapamycin (mTOR), a key regulatory kinase. In the presence of everolimus phosphorylation of p70 S6 ribosomal protein kinase (p70S6K), a substrate of mTOR, is inhibited. Consequently, phosphorylation of the ribosomal S6 protein and subsequent protein synthesis and cell proliferation are inhibited. The everolimus: FKBP-12 complex has no effect on calcineurin activity.

In rats and nonhuman primate models, everolimus effectively reduces kidney allograft rejection resulting in prolonged graft survival.

12.3 Pharmacokinetics

Everolimus pharmacokinetics have been characterized after oral administration of single and multiple doses to adult kidney transplant patients, hepatically-impaired patients, and healthy subjects.

Absorption

After oral dosing, peak everolimus concentrations occur 1 to 2 hours post dose. Over the dose range of 0.5 mg to 2 mg twice daily, everolimus Cmax and AUC are dose proportional in transplant patients at steady-state.

Food Effect

In 24 healthy subjects, a high-fat breakfast (44.5 g fat) reduced everolimus Cmax by 60%, delayed Tmax by a median 1.3 hours, and reduced AUC by 16% compared with a fasting administration. To minimize variability, everolimus should be taken consistently with or without food [see Dosage and Administration (2.6)].

Distribution

The blood-to-plasma ratio of everolimus is concentration dependent ranging from 17% to 73% over the range of 5 ng/mL to 5000 ng/mL. Plasma protein binding is approximately 74% in healthy subjects and in patients with moderate hepatic impairment. The apparent distribution volume associated with the terminal phase (Vz/F) from a single-dose pharmacokinetic study in maintenance kidney transplant patients is 342 to 107 L (range: 128 to 589 L).

Elimination

Metabolism

Everolimus is a substrate of CYP3A4 and P-gp. Following oral administration, everolimus is the main circulating component in human blood. Six main metabolites of everolimus have been detected in human blood, including 3 monohydroxylated metabolites, 2 hydrolytic ring-opened products, and a phosphatidylcholine conjugate of everolimus. These metabolites were also identified in animal species used in toxicity studies and showed approximately 100 times less activity than everolimus itself.

Excretion

After a single dose of radiolabeled everolimus was given to transplant patients receiving cyclosporine, the majority (80%) of radioactivity was recovered from the feces and only a minor amount (5%) was excreted in urine. Parent drug was not detected in urine and feces.

Pharmacokinetics in Kidney Transplant Patients

Steady-state is reached by Day 4 with an accumulation in blood concentrations of 2- to 3-fold compared with the exposure after the first dose. Table 4 below provides a summary of the steady-state pharmacokinetic parameters.

Table 4. Steady-State Pharmacokinetic Parameters (mean +/- SD) Following the Administration of 0.75 mg Twice Daily
Cmax | Tmax | AUC | CL/F^1 | Vc/F^1 | Half-life (T 1/2)
11.1 + 4.6 ng/mL | 1-2 h | 75 + 31 ng•h/mL | 8.8 L/h | 110 L | 30 ± 11 h
^1Population pharmacokinetic analysis.

The half-life estimates from 12 maintenance renal transplant patients who received single doses of everolimus capsules at 0.75 mg or 2.5 mg with their maintenance cyclosporine regimen indicate that the pharmacokinetics of everolimus are linear over the clinically-relevant dose range. Results indicate the half-life of everolimus in maintenance renal transplant patients receiving single doses of 0.75 mg or 2.5 mg Zortress during steady-state cyclosporine treatment was 30 ± 11 hours (range: 19 to 53 hours).

12.5 Drug-Drug Interactions

Everolimus is known to be a substrate for both cytochrome CYP3A4 and P-gp. The pharmacokinetic interaction between everolimus and concomitantly administered drugs is discussed below. Drug interaction studies have not been conducted with drugs other than those described below [see Warnings and Precautions (5.14), Drug Interactions (7)].

Cyclosporine (CYP3A4/P-gp Inhibitor and CYP3A4 Substrate): Zortress should be taken concomitantly with cyclosporine in kidney transplant patients. Everolimus concentrations may decrease when doses of cyclosporine are reduced, unless the Zortress dose is increased [see Dosage and Administration (2.1), Drug Interactions (7.2)].

In a single-dose study in healthy subjects, cyclosporine (Neoral) administered at a dose of 175 mg increased everolimus AUC by 168% (range: 46% to 365%) and Cmax by 82% (range: 25% to 158%) when administered with 2 mg Zortress compared with administration of Zortress alone [see Drug Interactions (7.2)].

Ketoconazole and Other Strong CYP3A4 Inhibitors: Multiple-dose administration of 200 mg ketoconazole twice daily for 5 days to 12 healthy volunteers significantly increased everolimus Cmax, AUC, and half-life by 3.9-fold, 15-fold, and 89%, respectively, when coadministered with 2 mg Zortress. It is recommended that strong inhibitors of CYP3A4 (e.g., ketoconazole, itraconazole, voriconazole, clarithromycin, telithromycin, ritonavir, boceprevir, telaprevir) should not be coadministered with Zortress [see Warnings and Precautions (5.14), Drug Interactions (7.3)].

Erythromycin (Moderate CYP3A4 Inhibitor): Multiple-dose administration of 500 mg erythromycin 3 times daily for 5 days to 16 healthy volunteers significantly increased everolimus Cmax, AUC, and half-life by 2-fold, 4.4-fold, and 39%, respectively, when coadministered with 2 mg Zortress. If erythromycin is coadministered, everolimus blood concentrations should be monitored and a dose adjustment made as necessary [see Drug Interactions (7.4)].

Verapamil (CYP3A4 Inhibitor and P-gp Substrate): Multiple-dose administration of 80 mg verapamil 3 times daily for 5 days to 16 healthy volunteers significantly increased everolimus Cmax and AUC by 2.3-fold and 3.5-fold, respectively, when coadministered with 2 mg Zortress. Everolimus half-life was not changed. If verapamil is coadministered, everolimus blood concentrations should be monitored and a dose adjustment made as necessary [see Drug Interactions (7.5)].

Atorvastatin (CYP3A4 Substrate) and Pravastatin (P-gp Substrate): Following administration of a single dose of 2 mg Zortress to 12 healthy subjects, the concomitant administration of a single oral dose administration of atorvastatin 20 mg or pravastatin 20 mg only slightly decreased everolimus Cmax and AUC by 9% and 10%, respectively. There was no apparent change in the mean T1/2 or median Tmax. In the same study, the concomitant Zortress dose slightly increased the mean Cmax of atorvastatin by 11% and slightly decreased the AUC by 7%. The concomitant Zortress dose decreased the mean Cmax and AUC of pravastatin by 10% and 5%, respectively. No dosage adjustments are needed for concomitant administration of Zortress and atorvastatin and pravastatin [see Drug Interactions (7.6)].

Midazolam (CYP3A4/5 Substrate): In 25 healthy male subjects, coadministration of a single dose of midazolam 4 mg oral solution with steady-state everolimus (10 mg daily dose for 5 days) resulted in a 25% increase in midazolam Cmax and a 30% increase in midazolam AUC; whereas the terminal half-life of midazolam and the metabolic AUC-ratio (1-hydroxymidazolam/midazolam) were not affected [see Drug Interactions (7.9)].

Rifampin (Strong CYP3A4 and P-gp Inducer): Pretreatment of 12 healthy subjects with multiple-dose rifampin (600 mg once-daily for 8 days) followed by a single dose of 4 mg Zortress increased everolimus clearance nearly 3-fold, and decreased Cmax by 58% and AUC by 63%. Combination with rifampin is not recommended [see Drug Interactions (7.8)].

12.6 Specific Populations

Hepatic Impairment

Relative to the AUC of everolimus in subjects with normal hepatic function, the average AUC in 6 patients with mild hepatic impairment (Child-Pugh Class A) was 1.6-fold higher following administration of a 10 mg single dose. In 2 independently studied groups of 8 and 9 patients with moderate hepatic impairment (Child-Pugh Class B) the average AUC was 2.1-fold and 3.3-fold higher following administration of a 2 mg or a 10 mg single dose, respectively; and in 6 patients with severe hepatic impairment (Child-Pugh Class C) the average AUC was 3.6-fold higher following administration of a 10 mg single dose. For patients with mild hepatic impairment (Child-Pugh Class A), the dose should be reduced by approximately one-third of the normally recommended daily dose. For patients with moderate or severe hepatic impairment (Child-Pugh Class B or C), the initial daily dose should be reduced to approximately one-half of the normally recommended daily dose. Further dose adjustment and/or dose titration should be made if a patient’s whole blood trough concentration of everolimus, as measured by an LC/MS/MS assay, is not within the target trough concentration range of 3 to 8 ng/mL [see Dosage and Administration (2.7)].

Renal Impairment

No pharmacokinetic studies in patients with renal impairment were conducted. Posttransplant renal function (creatinine clearance range: 11 to 107 mL/min) did not affect the pharmacokinetics of everolimus; therefore, no dosage adjustments are needed in patients with renal impairment.

Geriatrics

A limited reduction in everolimus oral CL/F of 0.33% per year was estimated in adults (age range studied was 16 to 70 years). There is no evidence to suggest that elderly patients will require a different dosage recommendation from younger adult patients.

Race

Based on analysis of population pharmacokinetics, oral clearance (CL/F) is, on average, 20% higher in black transplant patients.

12.7 Everolimus Whole Blood Concentrations Observed in Kidney and in Liver Transplant Patients

Everolimus in Kidney Transplantation

Based on exposure-efficacy and exposure-safety analyses of clinical trials and using an LC/MS/MS assay method, kidney transplant patients achieving everolimus whole blood trough concentrations greater than or equal to 3 ng/mL have been found to have a lower incidence of treated biopsy-proven acute rejection compared with patients whose trough concentrations were below 3 ng/mL. Patients who attained everolimus trough concentrations within the range of 6 to 12 ng/mL had similar efficacy and more adverse reactions than patients who attained lower trough concentrations between 3 to 8 ng/mL [see Dosage and Administration (2.3)].

In the kidney clinical trial [see Clinical Studies (14.1)], everolimus whole blood trough concentrations were measured at Days 3, 7, and 14 and Months 1, 2, 3, 4, 6, 7, 9, and 12. The proportion of patients receiving 0.75 mg twice daily Zortress treatment regimen who had everolimus whole blood trough concentrations within the protocol specified target range of 3 to 8 ng/mL at Days 3, 7, and 14 were 55%, 71% and 69%, respectively. Approximately 80% of patients had everolimus whole blood trough concentrations within the 3 to 8 ng/mL target range by Month 1 and remained stable within range through Month 12 posttransplant. The median everolimus trough concentration for the 0.75 mg twice daily treatment group was between 3 and 8 ng/mL throughout the study duration.

Everolimus in Liver Transplantation

In the liver clinical trial [see Clinical Studies (14.2)], Zortress dosing was initiated after 30 days following transplantation. Whole blood trough everolimus concentrations were measured within 5 days after first dose, followed by weekly intervals for 3 to 4 weeks, and then monthly thereafter. Approximately 49%, 37%, and 18% of patients, respectively, were below 3 ng/mL at 1, 2, and 4 weeks after initiation of Zortress dosing. The majority of patients (approximately 70% to 80%) had everolimus trough blood concentrations within the target range of 3 to 8 ng/mL from Month 2 through Month 24 posttransplant.

12.8 Cyclosporine Concentrations Observed in Kidney Transplant Patients

In the kidney transplant clinical trial [see Clinical Studies (14.1)], the target cyclosporine whole blood trough concentration for the Zortress treatment arm of 0.75 mg twice daily were 100 to 200 ng/mL through Month 1 posttransplant, 75 to 150 ng/mL at Months 2 and 3 posttransplant, 50 to 100 ng/mL at Month 4 posttransplant, and 25 to 50 ng/mL from Month 6 through Month 12 posttransplant. Table 5 below provides a summary of the observed cyclosporine whole blood trough concentrations during the study.

Table 5. Cyclosporine Trough Concentrations Over 12 Months Posttransplant – Kidney Study Median Values (ng/mL) With 10th and 90th Percentiles
Treatment Group | Visit | N | Target (ng/mL) | Median | 10 th percentile | 90 th percentile
Zortress 0.75 mg twice daily | Day 3 | 242 | 100-200 | 172 | 46 | 388
 | Day 7 | 265 | 100-200 | 185 | 75 | 337
 | Day 14 | 243 | 100-200 | 182 | 97 | 309
 | Month 1 | 245 | 100-200 | 161 | 85 | 274
 | Month 2 | 232 | 75-150 | 140 | 84 | 213
 | Month 3 | 220 | 75-150 | 111 | 68 | 187
 | Month 4 | 208 | 50-100 | 99 | 56 | 156
 | Month 6 | 200 | 25-50 | 75 | 43 | 142
 | Month 7 | 199 | 25-50 | 59 | 36 | 117
 | Month 9 | 194 | 25-50 | 49 | 28 | 91
 | Month 12 | 186 | 25-50 | 46 | 25 | 100

12.9 Tacrolimus Concentrations in Liver Transplant

In the liver transplant clinical trial [see Clinical Studies (14.2)], the target tacrolimus whole blood trough concentrations were greater than or equal to 8 ng/mL in the first 30 days posttransplant. The protocol required that patients had a tacrolimus trough concentration of at least 8 ng/mL in the week prior to initiation of Zortress. Zortress was initiated after 30 days posttransplant. At that time, the target tacrolimus trough concentrations were reduced to 3 to 5 ng/mL. Table 6 below provides a summary of the tacrolimus whole blood trough concentrations observed during the study through Month 24 posttransplant.

Table 6. Tacrolimus Trough Concentrations Over 24 Months Posttransplant – Liver Study Median Values (ng/mL) With 10th and 90th Percentiles
Treatment Group | Visit | N | Target (ng/mL) | Median | 10 th percentile | 90 th percentile
Pre-dose group Zortress 1 mg twice daily (initiated at Month 1) | Week 4 | 234 | 3 to 5 | 9.5 | 5.8 | 14.6
 | Week 5 | 219 | 3 to 5 | 8.1 | 4.5 | 13.8
 | Week 6 | 233 | 3 to 5 | 7.0 | 4.1 | 12.0
 | Month 2 | 219 | 3 to 5 | 5.6 | 3.4 | 10.3
 | Month 3 | 218 | 3 to 5 | 5.2 | 3.1 | 9.7
 | Month 4 | 196 | 3 to 5 | 4.9 | 2.9 | 7.7
 | Month 5 | 195 | 3 to 5 | 4.8 | 2.7 | 7.3
 | Month 6 | 200 | 3 to 5 | 4.6 | 3.0 | 7.5
 | Month 9 | 186 | 3 to 5 | 4.4 | 2.9 | 8.0
 | Month 12 | 175 | 3 to 5 | 4.3 | 2.6 | 7.3
 | Month 24 | 109 | 3 to 5 | 3.8 | 2.3 | 5.5

13 NONCLINICAL TOXICOLOGY

13.1 Carcinogenesis, Mutagenesis, Impairment of Fertility

Everolimus was not carcinogenic in mice or rats when administered daily by oral gavage for 2 years at doses up to 0.9 mg/kg, the highest dose tested. In these studies, AUCs in mice were higher (at least 20 times) than those in humans receiving 0.75 mg twice daily, and AUCs in rats were in the same range as those in humans receiving 0.75 mg twice daily.

Everolimus was not mutagenic in the bacterial reverse mutation, the mouse lymphoma thymidine kinase assay, or the chromosome aberration assay using V79 Chinese hamster cells, or in vivo following two daily doses of 500 mg/kg in the mouse micronucleus assay.

In a 13-week male fertility oral gavage study in rats, testicular morphology was affected at 0.5 mg/kg and above, and sperm motility, sperm head count and plasma testosterone concentrations were diminished at 5 mg/kg which caused a decrease in male fertility. There was evidence of reversibility of these findings in animals examined after 13 weeks post-dosing. The 0.5 mg/kg dose in male rats resulted in AUCs in the range of clinical exposures, and the 5 mg/kg dose resulted in AUCs approximately 5 times the AUCs in humans receiving 0.75 mg twice daily.

Oral doses of everolimus in female rats greater or equal to 0.1 mg/kg (approximately 0.13-fold the estimated AUC 0-24h in patients receiving the starting dose 0.75 mg twice daily) resulted in increased incidence of pre-implantation loss.

13.2 Animal Toxicology and/or Pharmacology

In an oral neonatal and juvenile development study in rats, oral administration of everolimus from postnatal Day 7 to 70 produced dose-related delayed attainment of developmental landmarks, including delayed eye-opening, delayed reproductive development in males and females, and increased latency time during the learning and memory phases were observed at doses as low as 0.15 mg/kg/day. Exposures in the rat at these doses were equal to or less than those obtained in adult human transplant patients.

14 CLINICAL STUDIES

14.1 Prevention of Organ Rejection After Kidney Transplantation

A 24-month, multi-national, open-label, randomized (1:1:1) trial was conducted comparing two concentration-controlled Zortress regimens of 1.5 mg per day starting dose (targeting 3 to 8 ng/mL using an LC/MS/MS assay method and 3 mg per day starting dose (targeting 6 to 12 ng/mL using an LC/MS/MS assay method) with reduced exposure cyclosporine and corticosteroids, to 1.44 g per day of mycophenolic acid with standard exposure cyclosporine and corticosteroids. The mean cyclosporine starting dose was 5.2, 5 and 5.7 mg/kg body weight/day in the Zortress 1.5 mg, 3 mg and in mycophenolic acid groups, respectively. The cyclosporine dose in the Zortress group was then adjusted to the blood trough concentration ranges indicated in Table 5, whereas in the mycophenolic acid group the target ranges were 200 to 300 ng/mL starting Day 5: 200 to 300 ng/mL, and 100 to 250 ng/mL from Month 2 to Month 12.

All patients received basiliximab induction therapy. The study population consisted of 18- to 70-year-old male and female low-to-moderate risk renal transplant recipients undergoing their first transplant. Low to moderate immunologic risk was defined in the study as an ABO blood type compatible first organ or tissue transplant recipient with anti-human leukocyte antigen (HLA) Class I panel reactive antibody (PRA) less than 20% by a complement dependent cytotoxicity-based assay, or less than 50% by a flow cytometry or ELISA-based assay, and with a negative T-cell cross match. Eight hundred thirty-three (833) patients were randomized after transplantation; 277 randomized to the Zortress 1.5 mg per day group, 279 to the Zortress 3 mg per day group and 277 to the mycophenolic acid 1.44 g per day group. The study was conducted at 79 renal transplant centers across Europe, South Africa, North and South America, and Asia-Pacific. There were no major baseline differences between treatment groups with regard to recipient or donor disease characteristics. The majority of transplant recipients in all groups (70% to 76%) had three or more HLA mismatches; mean percentage of panel reactive antibodies ranged from 1% to 2%. The rate of premature treatment discontinuation at 12 months was 30% and 22% in the Zortress 1.5 mg and control groups, respectively, (p = 0.03, Fisher’s exact test) and was more prominent between groups among female patients. Results at 12 months indicated that Zortress 1.5 mg per day is comparable to control with respect to efficacy failure, defined as treated biopsy-proven acute rejection*, graft loss, death, or loss to follow-up. The percentage of patients experiencing this endpoint and each individual variable in the Zortress and control groups is shown in Table 7.

Table 7. Efficacy Failure by Treatment Group (ITT Population) at 12 Months After Kidney Transplantation
 |  | Zortress (everolimus) 1.5 mg per day with reduced exposure CsA N = 277 n (%) | Mycophenolic acid 1.44 g per day with standard exposure CsA N = 277 n (%)
Efficacy endpoints^1
Efficacy failure endpoint^2 |  | 70 (25.3) | 67 (24.2)
Treated biopsy proven acute rejection |  | 45 (16.2) | 47 (17.0)
Death |  | 7 (2.5) | 6 (2.2)
Graft loss |  | 12 (4.3) | 9 (3.2)
Loss to follow-up |  | 12 (4.3) | 9 (3.2)
Graft loss or death or loss to follow-up^3 |  | 32 (11.6) | 26 (9.4)
Graft loss or death |  | 18 (6.5) | 15 (5.4)
Loss to follow-up^3 |  | 14 (5.1) | 11 (4.0)
Abbreviation: CsA, cyclosporine.
*Treated biopsy-proven acute rejection (tBPAR) was defined as a histologically confirmed acute rejection with a biopsy graded as IA, IB, IIA, IIB, or III according to 1997 Banff criteria that were treated with anti-rejection medication.
^1The difference in rates (Zortress–mycophenolic acid) with 95% confidence interval (CI) for primary efficacy failure endpoint is 1.1% (-6.1%, 8.3%); and for the graft loss, death or loss to follow-up endpoint is 2.2% (-2.9%, 7.3%).
^2Includes treated BPAR, graft loss, death or loss to follow-up by Month 12 where loss to follow-up represents patient who did not experience treated BPAR, graft loss or death and whose last contact date is prior to 12-month visit.
^3Loss to follow-up (for Graft Loss, Death, or Loss to Follow-up) represents patient who did not experience death or graft loss and whose last contact date is prior to 12-month visit.

The estimated mean glomerular filtration rate [using the Modification of Diet in Renal Disease (MDRD) equation] for Zortress 1.5 mg (target trough concentrations 3 to 8 ng/mL) and mycophenolic acid groups were comparable at Month 12 in the intent-to-treat (ITT) population (Table 8).

Table 8. Estimated Glomerular Filtration Rates (mL/min/1.73 m^2) by MDRD at 12 Months After Kidney Transplantation*
Month 12 GFR (MDRD) | Zortress (everolimus) 1.5 mg per day with reduced exposure CsA N = 276 | Mycophenolic acid 1.44 g per day with standard exposure CsA N = 277
Mean (SD) | 54.6 (21.7) | 52.3 (26.5)
Median (range) | 55.0 (0-140.9) | 50.1 (0.0-366.4)
Abbreviations: CsA, cyclosporine; MDRD, modification of diet in renal disease; SD, standard deviation.
*Analysis based on using a subject’s last observation carried forward for missing data at 12 months due to death or lost to follow-up data, a value of zero is used for subjects who experienced a graft loss.

Two earlier studies compared fixed doses of Zortress 1.5 mg per day and 3 mg per day, without TDM, combined with standard exposure cyclosporine and corticosteroids to mycophenolate mofetil 2 g per day and corticosteroids. Antilymphocyte antibody induction was prohibited in both studies. Both were multicenter, double-blind (for first 12 months), randomized trials (1:1:1) of 588 and 583 de novo renal transplant patients, respectively. The 12-month analysis of GFR showed increased rates of renal impairment in both the Zortress groups compared to the mycophenolate mofetil group in both studies. Therefore, reduced exposure cyclosporine should be used in combination with Zortress in order to avoid renal dysfunction and everolimus trough concentrations should be adjusted using TDM to maintain trough concentrations between 3 to 8 ng/mL [see Boxed Warning, Dosage and Administration (2.4), Warnings and Precautions (5.6)].

14.2 Prevention of Organ Rejection After Liver Transplantation

A 24-month, multinational, open-label, randomized (1:1:1) trial was conducted in liver transplant patients starting 30 days posttransplant. During the first 30 days, after transplant and prior to randomization, patients received tacrolimus and corticosteroids, with or without mycophenolate mofetil. No induction antibody was administered. Approximately 70% to 80% of patients received at least one dose of mycophenolate mofetil at a median total daily dose of 1.5 g during the first 30 days. For eligibility, patients had to have a tacrolimus trough concentration of at least 8 ng/mL in the week prior to randomization.

At randomization, mycophenolate mofetil was discontinued and patients were randomized to one of two Zortress treatment groups [initial dose of 1 mg twice per day (2 mg daily) and adjusted to target trough concentrations using an LC/MS/MS assay of 3 to 8 ng/mL] either with reduced exposure of tacrolimus (target trough whole blood concentrations of 3 to 5 ng/mL) or tacrolimus elimination. In the tacrolimus elimination group, at Month 4 posttransplant, once the everolimus trough concentrations were within the target range of 6 to 10 ng/mL, reduced exposure tacrolimus was eliminated. The Zortress with tacrolimus elimination group was discontinued early due to higher incidence of acute rejection. In the control group, patients received standard exposure tacrolimus (target trough whole blood concentrations of 8 to 12 ng/mL tapered to 6 to 10 ng/mL by Month 4 posttransplant). All patients received corticosteroids during the trial.

The study population consisted of 18- to 70-year-old male and female liver transplant recipients undergoing their first transplant, mean age was approximately 54 years, more than 70% of patients were male, and the majority of patients were Caucasian, with approximately 89% of patients per treatment group completing the study. Key stratification parameters of HCV status (31% to 32% HCV positive across groups) and renal function (mean baseline eGFR range 79 to 83 mL/min/1.73 m^2) were also balanced between groups.

A total of 1147 patients were enrolled into the run-in period of this trial. At 30 days posttransplant, a total 719 patients, who were eligible according to study inclusion/exclusion criteria, were randomized into 1 of 3 treatment groups: Zortress with reduced exposure tacrolimus; N = 245, Zortress with tacrolimus elimination (tacrolimus elimination group); N = 231, or standard dose/exposure tacrolimus (tacrolimus control); N = 243. The study was conducted at 89 liver transplant centers across Europe, including the United Kingdom and Ireland, North and South America, and Australia.

Key inclusion criteria were recipients 18 to 70 years of age, eGFR greater or equal to 30 mL/min/1.73 m^2, tacrolimus trough level of greater or equal to 8 ng/mL in the week prior to randomization, and the ability to take oral medication.

Key exclusion criteria were recipients of multiple solid organ transplants, history of malignancy (except hepatocellular carcinoma within Milan criteria), human immunodeficiency virus, and any surgical or medical condition which significantly alter the absorption, distribution, metabolism and excretion of study drug.

There were no major baseline differences between treatment groups with regard to recipient or donor disease characteristics. Mean MELD scores at time of transplantation, cold ischemia times (CIT), and ABO matching were similar across groups. Overall, the treatment groups were comparable with respect to the key determinants of liver transplantation.

The tacrolimus elimination group was stopped prematurely due to a higher incidence of acute rejection and adverse reactions leading to treatment discontinuation reported during the elimination phase of tacrolimus. Therefore, a treatment regimen of Zortress with tacrolimus elimination is not recommended.

Results up to 24 months are presented indicating that Zortress with reduced exposure tacrolimus is comparable to standard exposure tacrolimus with respect to efficacy failure, defined as treated biopsy-proven acute rejection, graft loss, death, or loss to follow-up throughout 12 to 24 months of treatment. The percentage of patients experiencing this endpoint and each individual variable in the Zortress and control group for each time interval is shown in Table 9.

Table 9. Efficacy Failure by Treatment Group (ITT Population) at 12 and 24 Months After Liver Transplantation
 | Zortress (everolimus) with reduced exposure tacrolimus N = 245 n (%) | Tacrolimus standard exposure N = 243 n (%)
Efficacy endpoints^1 at 12 months
Composite efficacy failure endpoint^1,^2 | 22 (9.0) | 33 (13.6)
Treated biopsy proven acute rejection* | 7 (2.9) | 17 (7.0)
Death | 13 (5.3) | 7 (2.9)
Graft loss | 6 (2.4) | 3 (1.2)
Loss to follow-up^2 | 4 (1.6) | 9 (3.7)
Graft loss or death or loss to follow-up | 18 (7.3) | 18 (7.4)
Graft loss or death | 14 (5.7) | 8 (3.3)
Loss to follow-up | 4 (1.6) | 10 (4.1)
Efficacy endpoints at 24 months
Composite efficacy failure endpoint^2 | 45 (18.4) | 53 (21.8)
Treated biopsy proven acute rejection | 11 (4.5) | 18 (7.4)
Death | 17 (6.9) | 11 (4.5)
Graft loss | 9 (3.7) | 7 (2.9)
Loss to follow-up^2 | 18 (7.3) | 23 (9.5)
Graft loss or death or loss to follow-up^3 | 38 (15.5) | 39 (16.0)
Graft loss or death | 20 (8.2) | 15 (6.2)
Loss to follow-up^3 | 18 (7.3) | 24 (9.9)
*Treated biopsy-proven acute rejection (tBPAR) was defined as histologically confirmed acute rejection with a rejection activity index (RAI) greater than or equal to RAI score 3 that received anti-rejection treatment.
^1The difference in rates (Zortress – control) at 12 months with 97.5% CI for efficacy failure endpoint based on normal approximation with Yates continuity correction is -4.6% (-11.4%, 2.2%); and for the graft loss, death or loss to follow-up endpoint is -0.1% (-5.4%, 5.3%).
^2Loss to follow-up (for treated BPAR, graft loss, death or loss to follow-up) represents patients who did not experience treated BPAR, graft loss or death and whose last contact date is prior to 12- or 24-month visit.
^3Loss to follow-up (for graft loss, death, or loss to follow-up) represents patients who did not experience death or graft loss and whose last contact date is prior to 12- or 24-month visit.

At Month 12, the estimated mean glomerular filtration rate (eGFR) using the MDRD equation for the Zortress group was 80.9 mL/min/1.73 m^2 and the tacrolimus control was 70.3 mL/min/1.73 m^2 in the ITT population. At Month 24, the eGFR using the MDRD equation for the Zortress group was 74.7 mL/min/1.73 m^2 and for the tacrolimus control the eGFR was 67.8 mL/min/1.73 m^2 (Table 10).

Table 10. Estimated Glomerular Filtration Rates (mL/min/1.73 m^2) by MDRD at 12 and 24 Months After Liver Transplantation
e GFR (MDRD) | Zortress (everolimus) with reduced exposure tacrolimus | Tacrolimus standard exposure
Month 12 | N = 215 | N = 209
Mean (SD) | 80.9 (27.3) | 70.3 (23.1)
Median (range) | 78.3 (28.4-153.1) | 66.4 (27.9-155.8)
Month 24 | N = 184 | N = 186
Mean (SD) | 74.7 (26.1) | 67.8 (21.0)
Median (range) | 72.9 (20.3-151.6) | 65.2 (27.0-148.9)
Abbreviations: eGFR, Estimated Glomerular Filtration Rates; MDRD, Modification Of Diet In Renal Disease; SD, standard deviation.

Figure 1. Mean and 95% CI of eGFR (MDRD 4) [mL/min/1.73 m^2] by Visit Window and Treatment After Liver Transplantation (ITT population –- 24-Month Analysis)*

*Zortress dosing was initiated 30 days after transplantation.

Although the initial protocol was designed for 24 months, the study was subsequently extended to 36 months. One hundred six (106) patients (43%) in the Zortress group and 125 patients (51%) in the control group participated in the extension study from Month 24 to Month 36 after transplantation. The results for the Zortress group at 36 months were consistent with the results at 24 months in terms of tBPAR, graft loss, death, and eGFR.

16 HOW SUPPLIED/STORAGE AND HANDLING

Zortress (everolimus) tablets are packed in child-resistant blisters.

Table 11. Description of Zortress (everolimus) Tablets
Dosage strength | 0.25 mg | 0.5 mg | 0.75 mg | 1 mg
Appearance | White to yellowish, marbled, round, flat tablets with beveled edge
Imprint | “C” on one side and “NVR” on the other | “CH” on one side and “NVR” on the other | “CL” on one side and “NVR” on the other | “CU” on one side and “NVR” on the other
NDC number | 0078-0417-20 | 0078-0414-20 | 0078-0415-20 | 0078-0422-20

Each strength is available in boxes of 60 tablets (6 blister strips of 10 tablets each).

Storage

Store at 20°C to 25°C (68°F to 77°F); excursions permitted between 15°C and 30°C (59°F and 86°F) [see USP Controlled Room Temperature].

Protect from light and moisture.

17 PATIENT COUNSELING INFORMATION

Advise the patient to read the FDA-approved patient labeling (Medication Guide).

Administration

Inform patients that Zortress should be taken orally twice a day approximately 12 hours apart consistently either with or without food.

Inform patients to avoid grapefruit and grapefruit juice, which increase blood drug concentrations of Zortress [see Warnings and Precautions (5.20)].

Advise patients that Zortress should be used concurrently with reduced doses of cyclosporine and that any change in doses of these medications should be made under physician supervision. A change in the cyclosporine dose may also require a change in the dosage of Zortress.

Inform patients of the necessity of repeated laboratory tests according to physician recommendations while they are taking Zortress.

Development of Lymphomas and Other Malignancies

Inform patients they are at risk of developing lymphomas and other malignancies, particularly of the skin, due to immunosuppression. Advise patients to limit exposure to sunlight and ultraviolet (UV) light by wearing protective clothing and using a sunscreen with a high protection factor [see Warnings and Precautions (5.2)].

Increased Risk of Infection

Inform patients they are at increased risk of developing a variety of infections, including opportunistic infections, due to immunosuppression. Advise patients to contact their physician if they develop any symptoms of infection [see Warnings and Precautions (5.3, 5.13)].

Kidney Graft Thrombosis

Inform patients that Zortress has been associated with an increased risk of kidney arterial and venous thrombosis, resulting in graft loss, usually within the first 30 days posttransplantation [see Warnings and Precautions (5.4)].

Zortress and Calcineurin Inhibitor-Induced Nephrotoxicity

Advise patients of the risks of impaired kidney function with the combination of Zortress and cyclosporine as well as the need for routine blood concentration monitoring for both drugs. Advise patients of the importance of serum creatinine monitoring [see Warnings and Precautions (5.6)].

Angioedema

Inform patients of the risk of angioedema and that concomitant use of ACE inhibitors may increase this risk. Advise patients to seek prompt medical attention if symptoms occur [see Warnings and Precautions (5.8)].

Wound Healing Complications and Fluid Accumulation

Inform patients that the use of Zortress has been associated with impaired or delayed wound healing, fluid accumulation and the need for careful observation of their incision site [see Warnings and Precautions (5.9)].

Interstitial Lung Disease (ILD)/Non-Infectious Pneumonitis

Inform patients that the use of Zortress may increase the risk of non-infectious pneumonitis. Advise patients to seek medical attention if they develop clinical symptoms consistent with pneumonia [see Warnings and Precautions (5.10)].

Hyperlipidemia

Inform patients that the use of Zortress has been associated with increased serum cholesterol and triglycerides that may require treatment and the need for monitoring of blood lipid concentrations [see Warnings and Precautions (5.11)].

Proteinuria

Inform patients that the use of Zortress has been associated with an increased risk of proteinuria [see Warnings and Precautions (5.12)].

Pregnancy and Lactation

Advise women of childbearing age to avoid becoming pregnant throughout treatment and for 8 weeks after Zortress therapy has stopped. Zortress can cause fetal harm if taken during pregnancy. Advise a pregnant woman of the potential risk to a fetus. Also advise not to breastfeed while taking Zortress [see Use in Specific Populations (8.1, 8.2)].

Male and Female Fertility

Inform male and female patients that Zortress may impair fertility [see Warnings and Precautions (5.18), Use in Specific Populations (8.1, 8.3), Nonclinical Toxicology (13.1)].

Medications That Interfere With Zortress

Some medications can increase or decrease blood concentrations of Zortress. Advise patients to inform their physician if they are taking any of the following: antifungals, antibiotics, antivirals, anti-epileptic medicines including carbamazepine, phenytoin and barbiturates, herbal/dietary supplements (St. John’s Wort), cannabidiol, and/or rifampin [see Warnings and Precautions (5.14, 5.22)].

New Onset Diabetes

Inform patients that the use of Zortress may increase the risk of diabetes mellitus and to contact their physician if they develop symptoms [see Warnings and Precautions (5.16)].

Immunizations

Inform patients that vaccinations may be less effective while they are being treated with Zortress. Advise patients that live vaccines should be avoided [see Warnings and Precautions (5.19)].

Patient With Hereditary Disorders

Advise patients to inform their physicians that if they have hereditary disorders of galactose intolerance (Lapp-lactase deficiency or glucose-galactose malabsorption) not to take Zortress [see Warnings and Precautions (5.21)].

Distributed by:
Novartis Pharmaceuticals Corporation
East Hanover, New Jersey 07936

© Novartis

T2024-12

MEDICATION GUIDE
ZORTRESS [ZOR-tres]
(everolimus)
tablets, for oral use

What is the most important information I should know about ZORTRESS?

ZORTRESS can cause serious side effects, including:

- Increased risk of getting certain cancers. People who take ZORTRESS have a higher chance of getting lymphoma and other cancers, especially skin cancer. Talk to your doctor about your risk for cancer.
- Increased risk of serious infections. ZORTRESS weakens the body’s immune system and affects your ability to fight infections. Serious infections can happen with ZORTRESS that may lead to death. People taking ZORTRESS have a higher chance of getting infections caused by viruses, bacteria, and fungi (yeast).
  - Call your doctor if you have symptoms of infection, including fever or chills.

- Blood clot in the blood vessels of your transplanted kidney. If this happens, it usually occurs within the first 30 days after your kidney transplant. Tell your doctor right away if you:
  - have pain in your groin, lower back, side or stomach (abdomen)
  - make less urine or you do not pass any urine
  - have blood in your urine or dark colored urine (tea-colored)
  - have fever, nausea, or vomiting
- Serious problems with your transplanted kidney (nephrotoxicity). You will need to start with a lower dose of cyclosporine when you take it with ZORTRESS. Your doctor should do regular blood tests to check your levels of both ZORTRESS and cyclosporine.
- Increased risk of death that can be related to infection, in people who have had a heart transplant.
  You should not take ZORTRESS without talking to your doctor if you have had a heart transplant.

See the section “What are the possible side effects of ZORTRESS?” for information about other serious side effects.

What is ZORTRESS?

ZORTRESS is a prescription medicine used to prevent transplant rejection (antirejection medicine) in people who have received a kidney transplant or liver transplant. Transplant rejection happens when the body’s immune system perceives the new transplanted kidney or liver as “foreign” and attacks it.

ZORTRESS is used with other medicines called cyclosporine, corticosteroids and certain other transplant medicines to prevent rejection of your transplanted kidney. ZORTRESS is used with other medicines called tacrolimus and corticosteroids to prevent rejection of your transplanted liver.

It is not known if ZORTRESS is safe and effective in transplanted organs other than the kidney and liver.

It is not known if ZORTRESS is safe and effective in children under 18 years of age.

Do not take ZORTRESS if you are allergic to:

- everolimus (ZORTRESS/AFINITOR®) or any of the ingredients in ZORTRESS. See the end of this Medication Guide for a complete list of ingredients in ZORTRESS.
- sirolimus (Rapamune®)

Before taking ZORTRESS, tell your doctor about all of your medical conditions, including if you:

- have liver problems
- have skin cancer or it runs in your family
- have high cholesterol or triglycerides (fat in your blood)
- have Lapp lactase deficiency or glucose-galactose malabsorption. You should not take ZORTRESS if you have this disorder.
- are pregnant or could become pregnant. ZORTRESS may harm your unborn baby. If you are able to become pregnant, you should use effective birth control during treatment and for 8 weeks after your last dose of ZORTRESS. Talk to your doctor about birth control methods that may be right for you during this time. If you become pregnant or think you are pregnant, tell your healthcare provider right away. You should not become pregnant during treatment with ZORTRESS.
- are breastfeeding or plan to breastfeed. It is not known if ZORTRESS passes into your breast milk.

Tell your doctor about all the medicines you take, including prescription and over-the-counter medicines, vitamins, and herbal supplements.

Especially tell your doctor if you take:

- antifungal medicine
- antibiotic medicine
- heart medicine
- high blood pressure medicine
- a medicine to lower cholesterol or triglycerides
- cyclosporine (Sandimmune®, Gengraf®, Neoral®)
- tuberculosis (TB) medicine
- HIV medicine
- St. John’s Wort
- seizure (anticonvulsant) medicine
- cannabidiol (Epidiolex®)

How should I take ZORTRESS?

- Take ZORTRESS exactly as your doctor tells you to.
- Do not stop taking ZORTRESS or change your dose unless your doctor tells you to.
- Take ZORTRESS at the same time as your dose of cyclosporine or tacrolimus medicine.
- Do not stop taking or change your dose of cyclosporine or tacrolimus medicine unless your doctor tells you to.
- If your doctor changes your dose of cyclosporine or tacrolimus, your dose of ZORTRESS may change.
- Take ZORTRESS 2 times a day about 12 hours apart.
- Swallow ZORTRESS tablets whole with a glass of water. Do not crush or chew ZORTRESS tablets.
- Take ZORTRESS tablets with or without food. If you take ZORTRESS tablets with food, always take ZORTRESS tablets with food. If you take ZORTRESS tablets without food, always take ZORTRESS tablets without food.
- Your doctor will do regular blood tests to check your kidney or liver function while you take ZORTRESS. It is important that you get these tests done when your doctor tells you to. Blood tests will monitor how your kidneys or liver are working and make sure you are getting the right dose of ZORTRESS and other transplant medications you may be on (cyclosporine or tacrolimus).
- If you take too much ZORTRESS, call your doctor or go to the nearest hospital emergency room right away.

What should I avoid while taking ZORTRESS?

- Avoid receiving any live vaccines while taking ZORTRESS. Some vaccines may not work as well while you are taking ZORTRESS.
- Do not eat grapefruit or drink grapefruit juice while you are taking ZORTRESS. Grapefruit may increase your blood level of ZORTRESS.
- Limit the amount of time you spend in the sunlight. Avoid using tanning beds or sunlamps. People who take ZORTRESS have a higher risk of getting skin cancer. See the section “What is the most important information I should know about ZORTRESS?” Wear protective clothing when you are in the sun and use a sunscreen with a high protection factor (SPF 30 and above). This is especially important if you have fair skin or if you have a family history of skin cancer.
- Avoid becoming pregnant. See the section “What should I tell my doctor before taking ZORTRESS?”

What are the possible side effects of ZORTRESS?

ZORTRESS may cause serious side effects, including:

- See “What is the most important information I should know about ZORTRESS?”
- swelling under your skin especially around your mouth, eyes and in your throat (angioedema). Your chance of having swelling under your skin is higher if you take ZORTRESS along with certain other medicines. Tell your doctor right away or go to the nearest emergency room if you have any of these symptoms of angioedema:
  - sudden swelling of your face, mouth, throat, tongue or hands
  - hives or welts
  - itchy or painful swollen skin
  - trouble breathing
- delayed wound healing. ZORTRESS can cause your incision to heal slowly or not heal well. Call your doctor right away if you have any of the following symptoms:
  - your incision is red, warm or painful
  - blood, fluid, or pus in your incision
  - your incision opens up
  - swelling of your incision
- lung or breathing problems. Tell your doctor right away if you have new or worsening cough, shortness of breath, difficulty breathing or wheezing. In some patients, lung or breathing problems have been severe and can even lead to death. Your doctor may need to stop ZORTRESS or lower your dose.
- increased cholesterol and triglycerides (fat in your blood). If your cholesterol and triglyceride levels are high, your doctor may want to lower them with diet, exercise and certain medicines.
- protein in your urine (proteinuria).
- change in kidney function. ZORTRESS may cause kidney problems when taken along with a standard dose of cyclosporine medicine instead of a lower dose.

Your doctor should do blood and urine tests to monitor your cholesterol, triglycerides and kidney function.

- viral infections. Certain viruses can live in your body and cause active infections when your immune system is weak. Viral infections that can happen with ZORTRESS include BK virus-associated nephropathy. BK virus can affect how your kidney works and cause your transplanted kidney to fail.
- blood clotting problems. Talk to your doctor if this is a concern for you.
- diabetes. Tell your doctor if you have frequent urination, increased thirst or hunger.
- infertility, male. ZORTRESS can affect fertility in males and may affect your ability to father a child. Talk with your doctor if this is a concern for you.
- infertility, female. ZORTRESS can affect fertility in females and may affect your ability to become pregnant. Talk to your doctor if this is a concern for you.

The most common side effects of ZORTRESS in people who have had a kidney or liver transplant include:

These common side effects have been reported in both kidney and liver transplant patients:

- nausea
- swelling of the lower legs, ankles and feet
- high blood pressure

The most common side effects of ZORTRESS in people who have had a kidney transplant include:

- constipation
- low red blood cell count (anemia)
- urinary tract infection
- increased fat in the blood (cholesterol and triglycerides)

The most common side effects of ZORTRESS in people who have had a liver transplant include:

- diarrhea
- headache
- fever
- abdominal pain
- low white blood cells

These are not all of the possible side effects of ZORTRESS.

Call your doctor for medical advice about side effects. You may report side effects to FDA at 1-800-FDA-1088.

How should I store ZORTRESS?

- Store ZORTRESS tablets between 59°F and 86°F (15°C and 30°C).
- Keep ZORTRESS out of the light.
- Keep ZORTRESS tablets dry.

Keep ZORTRESS and all medicines out of the reach of children.

General information about the safe and effective use of ZORTRESS.

Medicines are sometimes prescribed for purposes other than those listed in a Medication Guide. Do not use ZORTRESS for a condition for which it was not prescribed. Do not give ZORTRESS to other people, even if they have the same symptoms that you have. It may harm them. You can ask your doctor or pharmacist for information about ZORTRESS that is written for healthcare professionals.

What are the ingredients in ZORTRESS?

Active ingredient: everolimus

Inactive ingredients: butylated hydroxytoluene, crospovidone, hypromellose, lactose anhydrous, lactose monohydrate, and magnesium stearate.

Distributed by:
Novartis Pharmaceuticals Corporation
East Hanover, New Jersey 07936

Rapamune® is a registered trademark of Pfizer Inc; Gengraf® is a registered trademark of Abbott Laboratories.

For more information, call 1-888-669-6682 or visit www.zortress.com.

This Medication Guide has been approved by the U.S. Food and Drug Administration.

Revised: February 2024

T2024-13

PRINCIPAL DISPLAY PANEL

NDC 0078-0417-20

Rx only

ZORTRESS®

(everolimus) Tablets

0.25 mg per tablet

Contents:
6 blister cards of
10 tablets each

DISPENSE WITH MEDICATION GUIDE
ENCLOSED OR PROVIDED SEPARATELY.

NOVARTIS

PRINCIPAL DISPLAY PANEL

NDC 0078-0414-20

Rx only

ZORTRESS®

(everolimus) Tablets

0.5 mg per tablet

Contents:
6 blister cards of
10 tablets each

DISPENSE WITH MEDICATION GUIDE
ENCLOSED OR PROVIDED SEPARATELY.

NOVARTIS

PRINCIPAL DISPLAY PANEL

NDC 0078-0415-20

Rx only

ZORTRESS®

(everolimus) Tablets

0.75 mg per tablet

Contents:
6 blister cards of
10 tablets each

DISPENSE WITH MEDICATION GUIDE
ENCLOSED OR PROVIDED SEPARATELY.

NOVARTIS

PRINCIPAL DISPLAY PANEL

NDC 0078-0422-20

Rx only

ZORTRESS®

(everolimus) Tablets

1 mg per tablet

Contents:
6 blister cards of
10 tablets each

DISPENSE WITH MEDICATION GUIDE
ENCLOSED OR PROVIDED SEPARATELY.

NOVARTIS